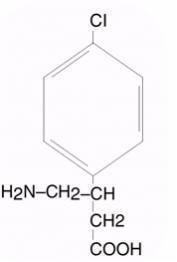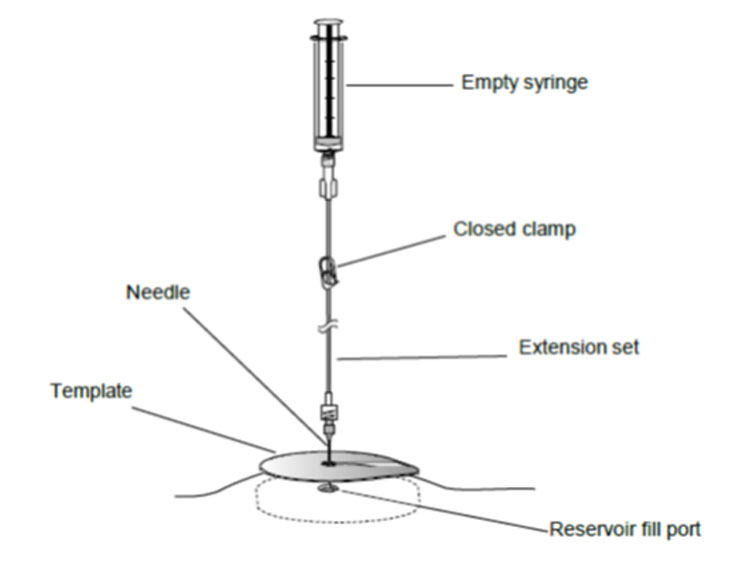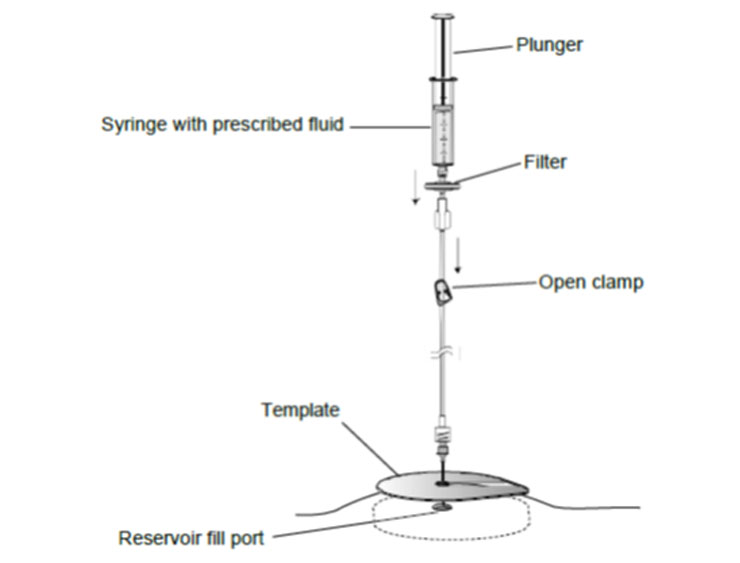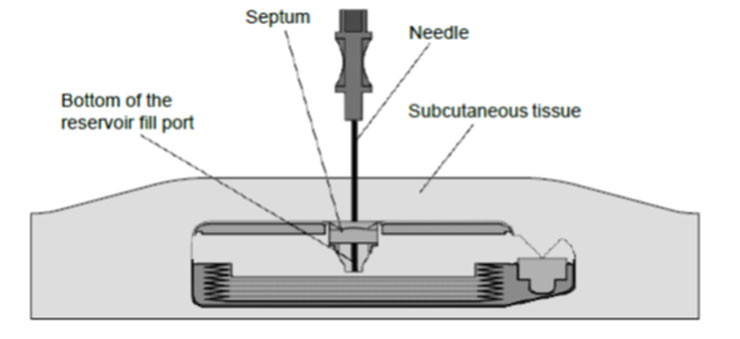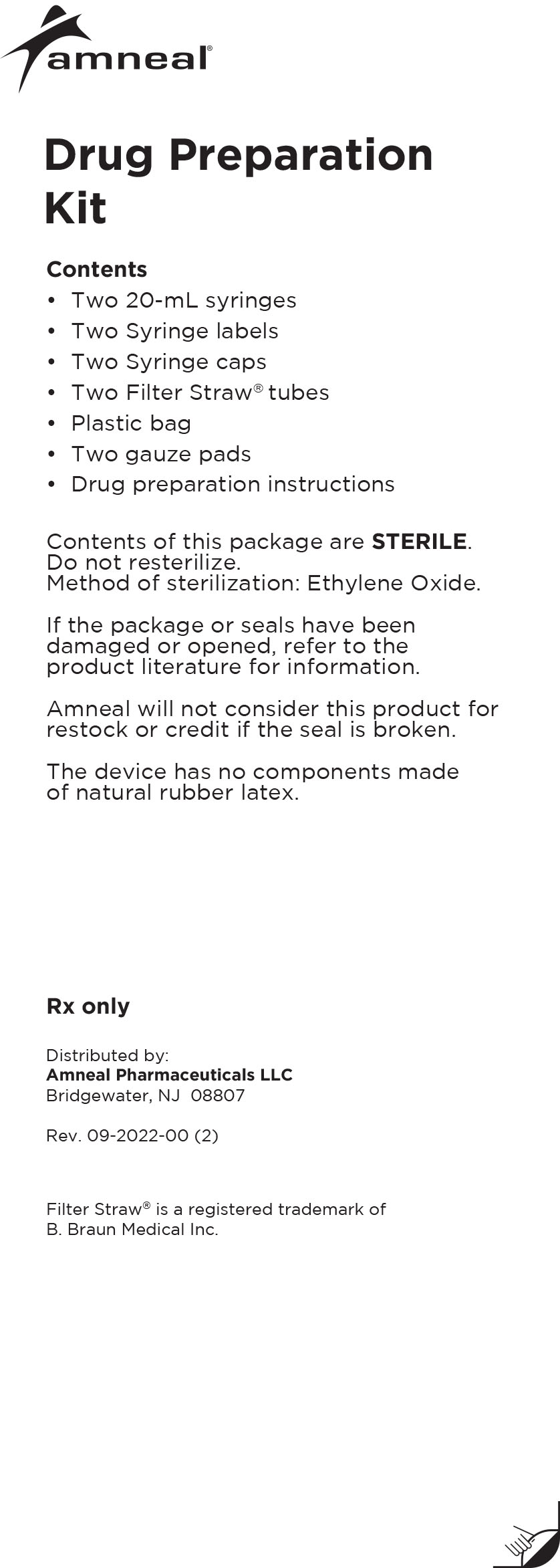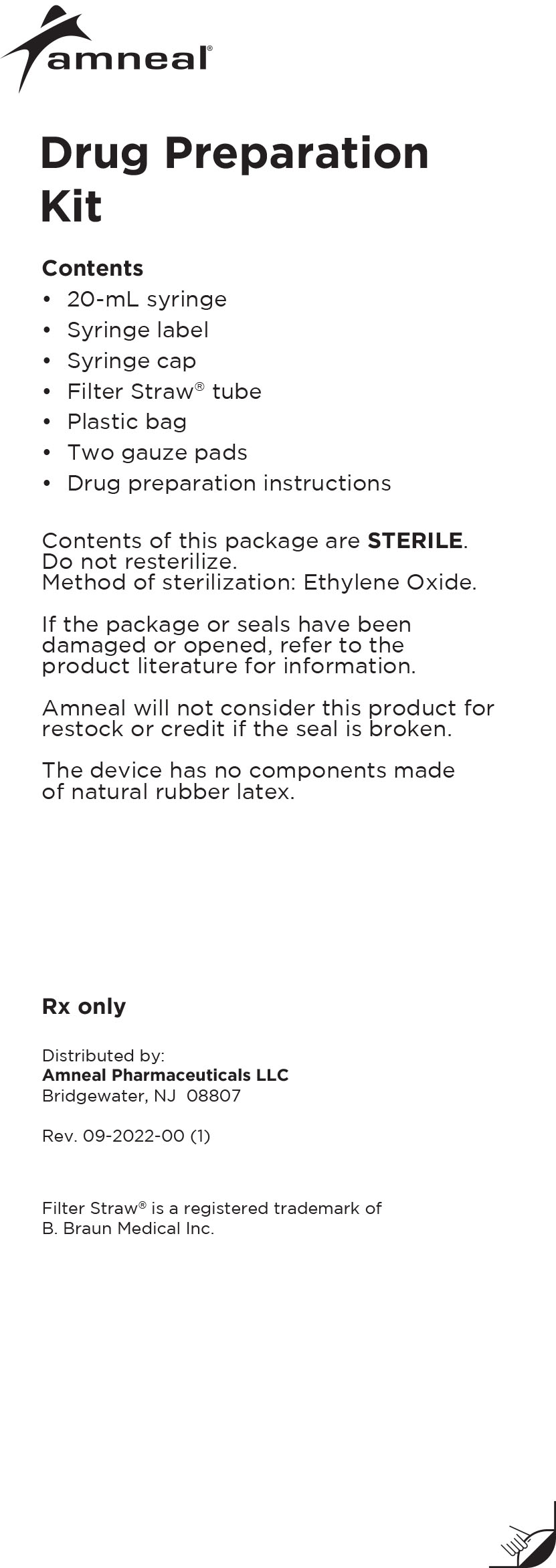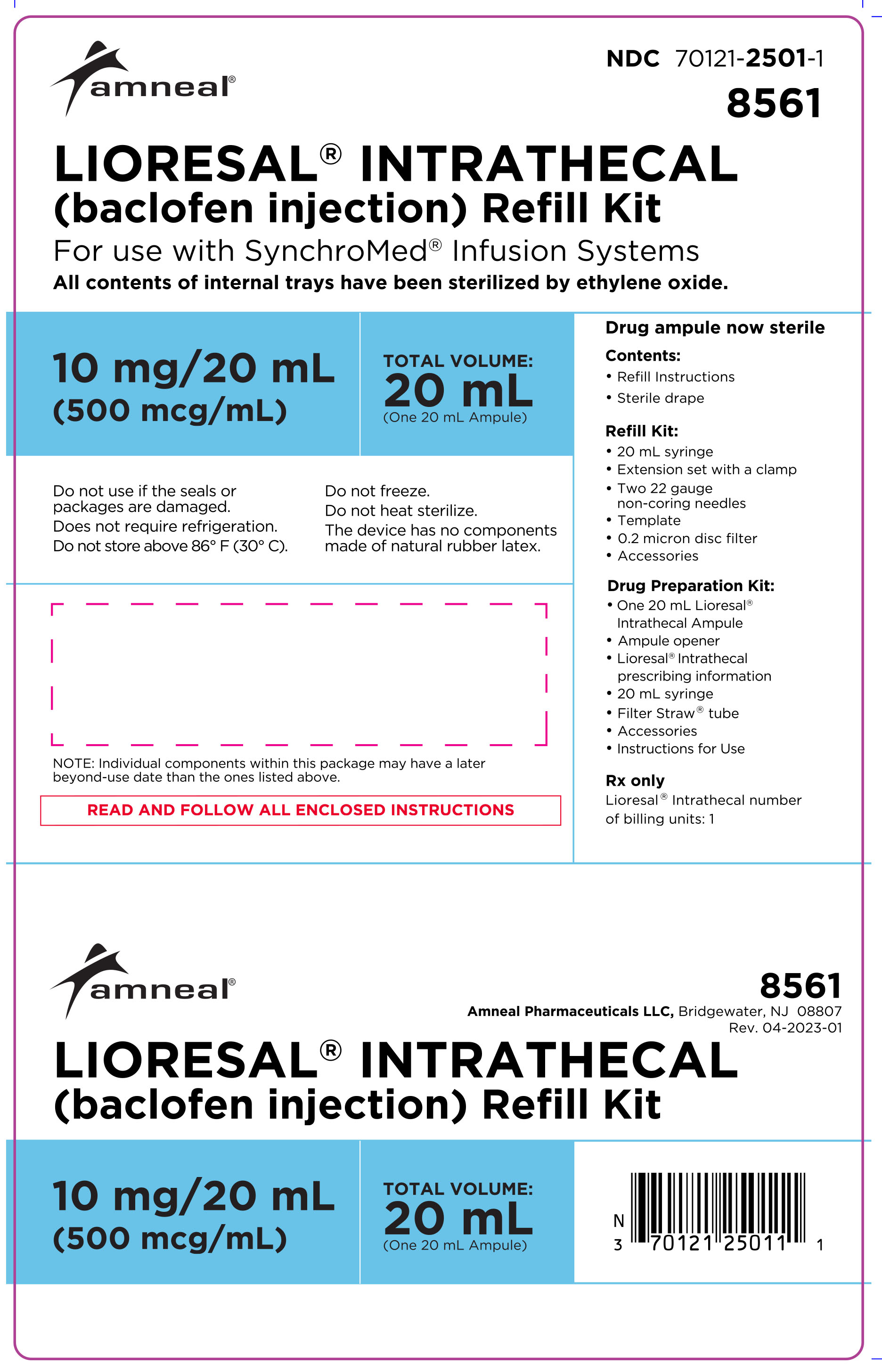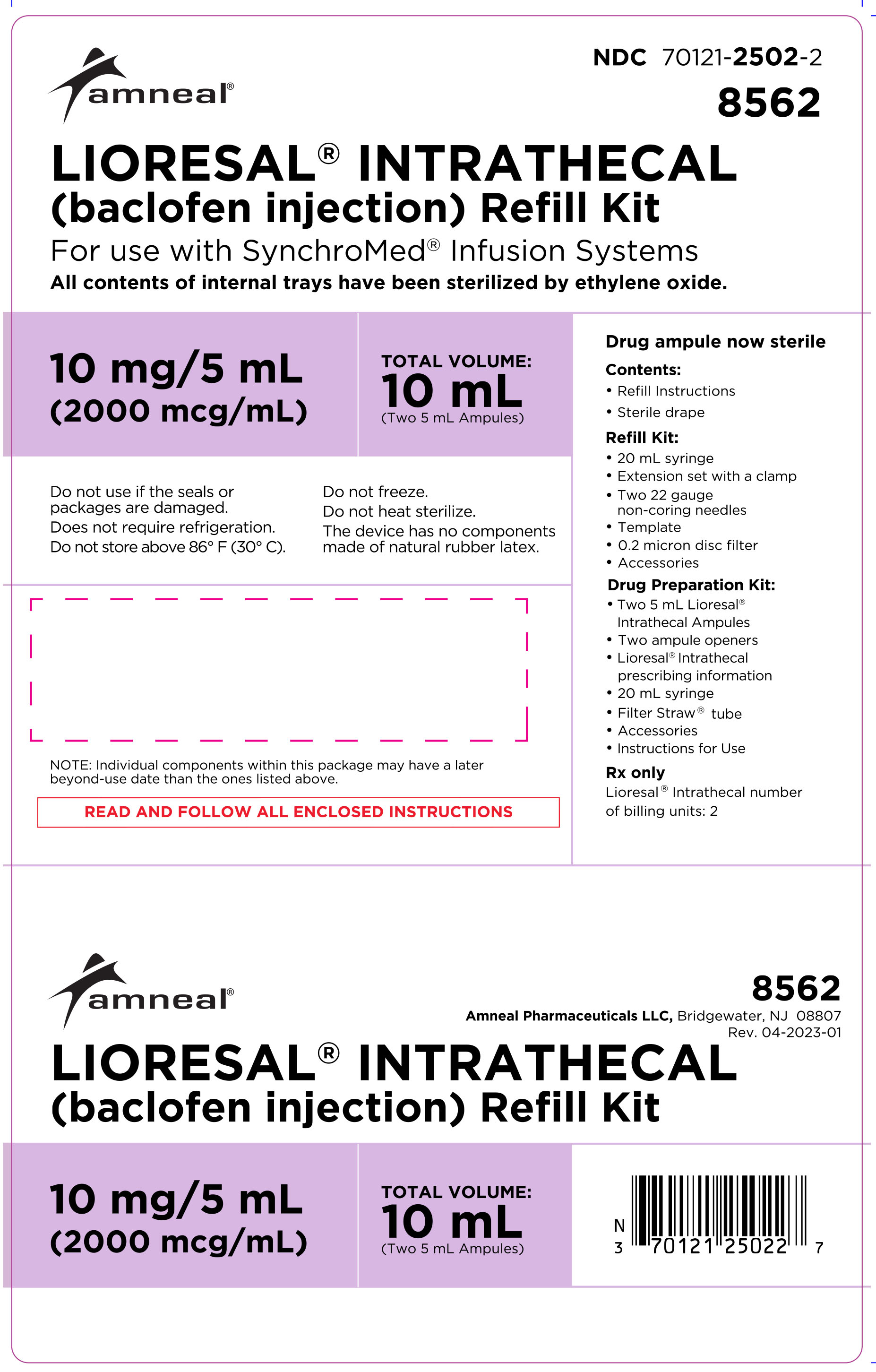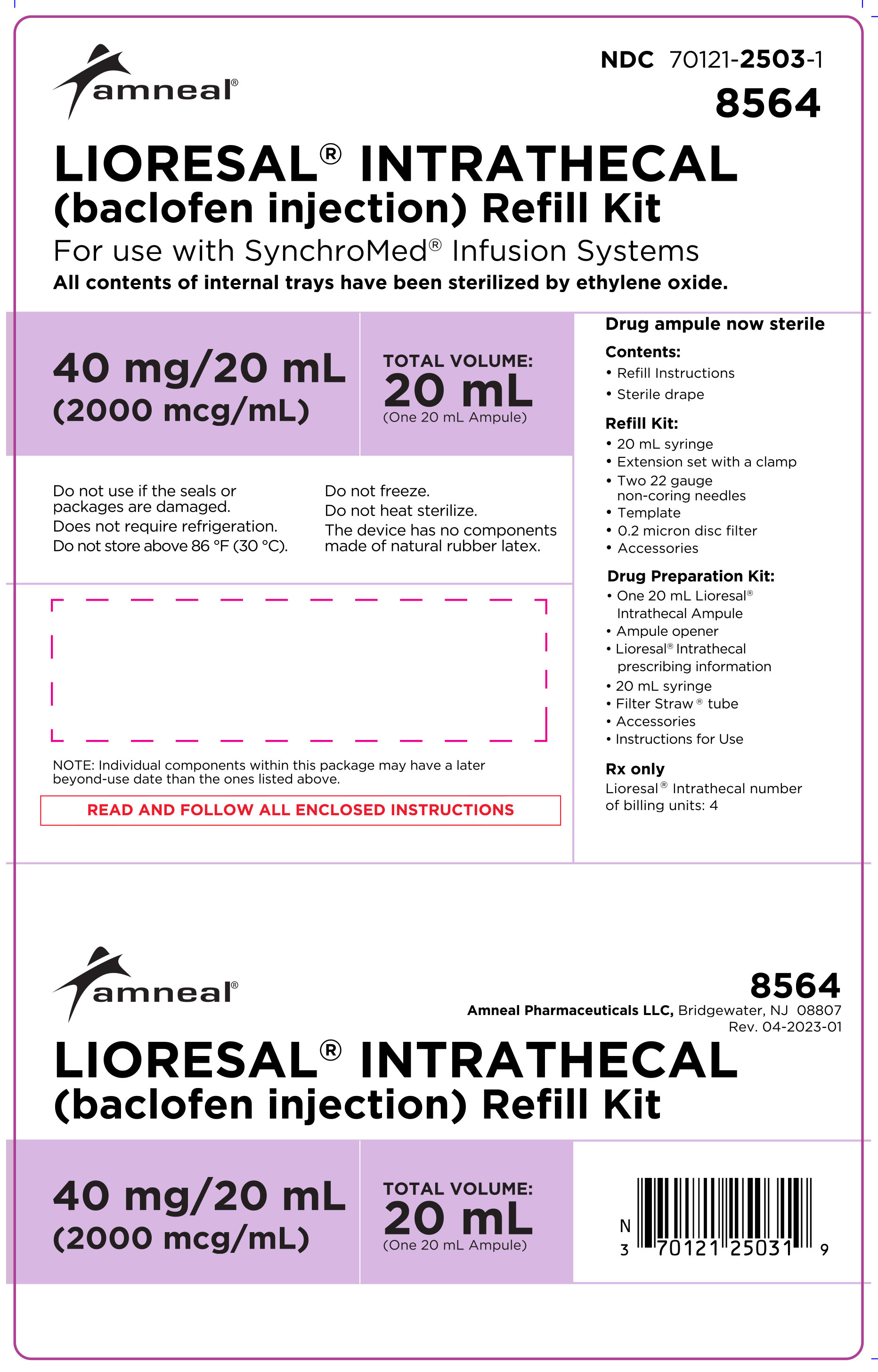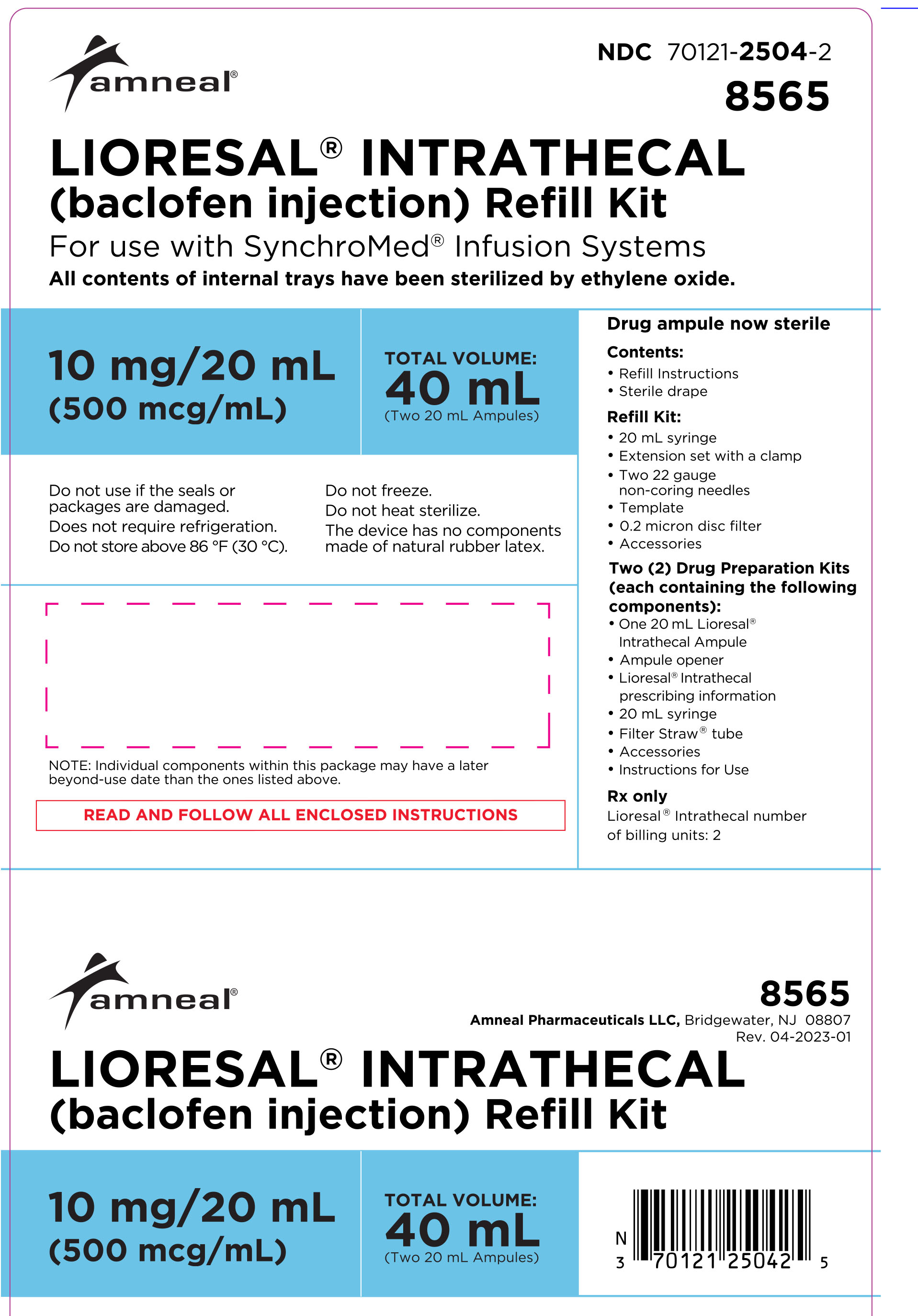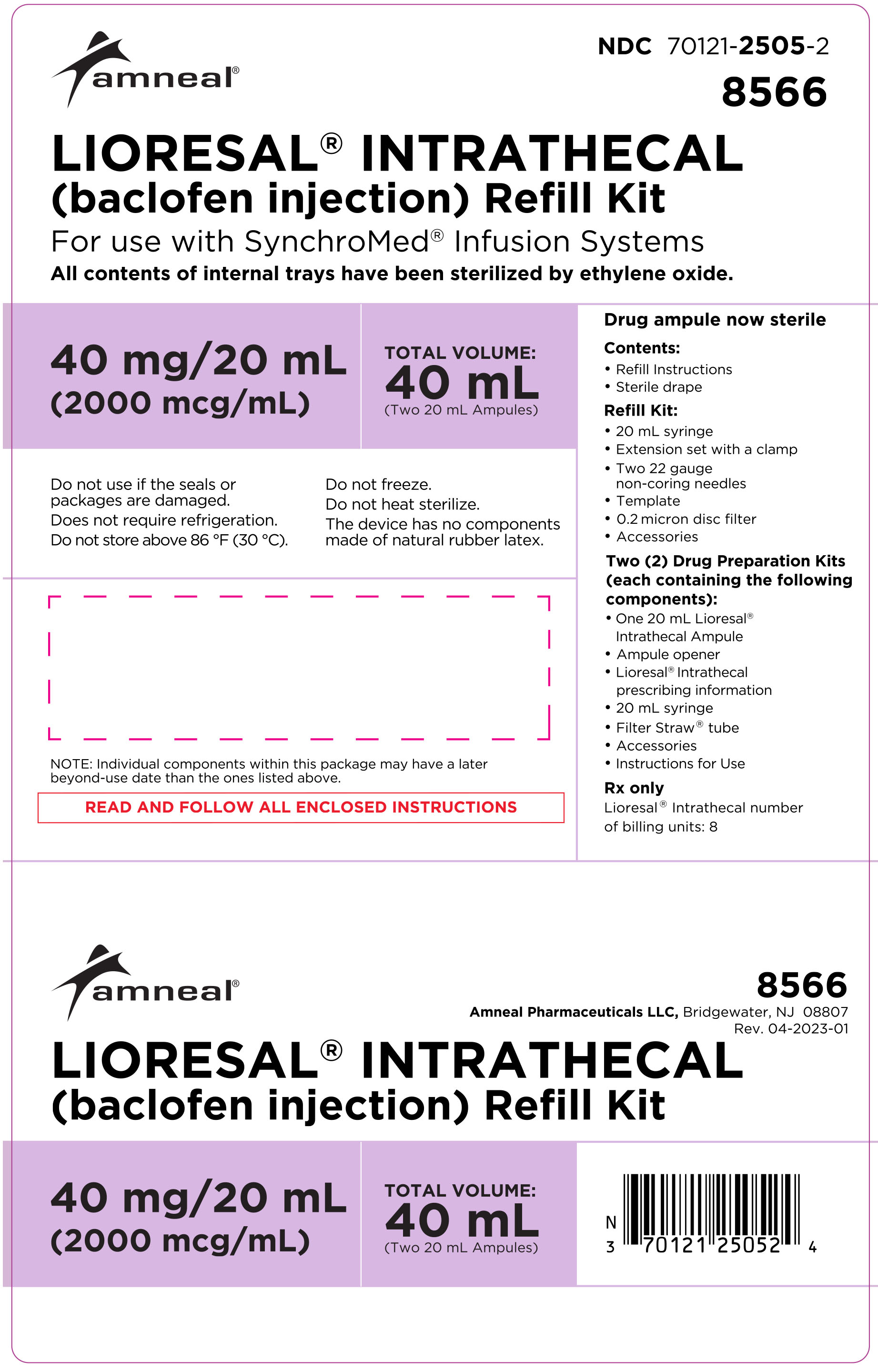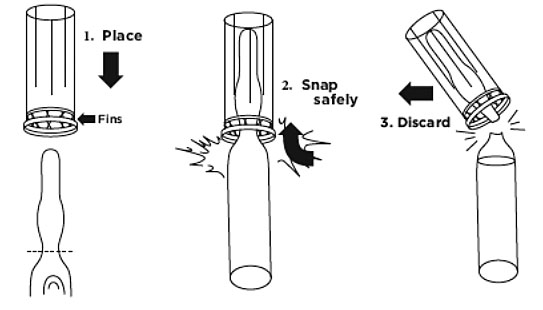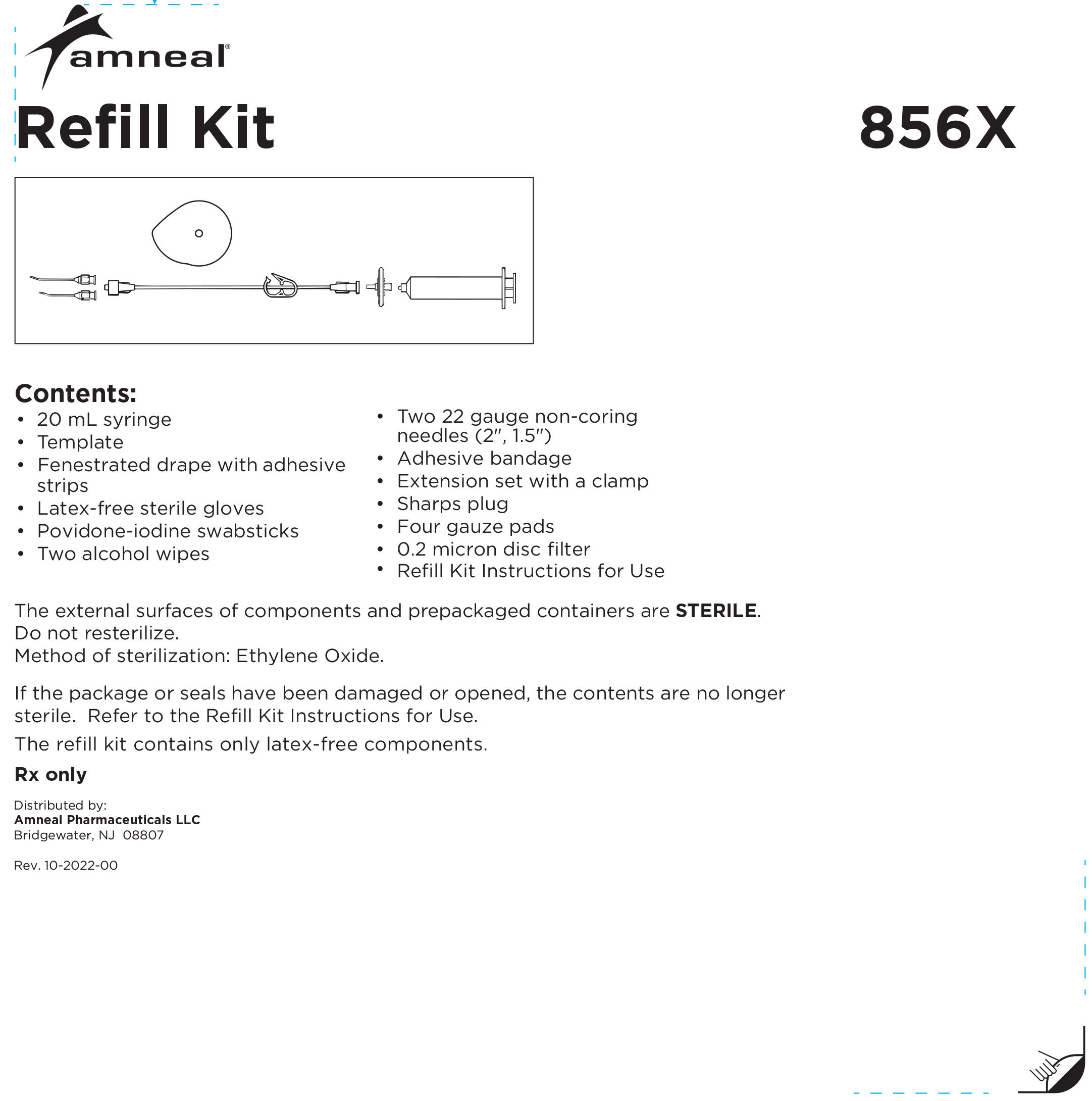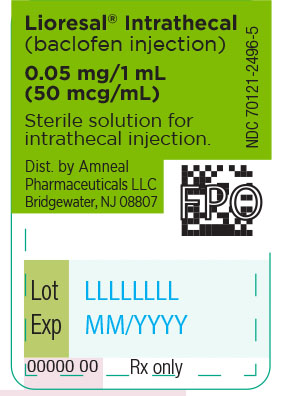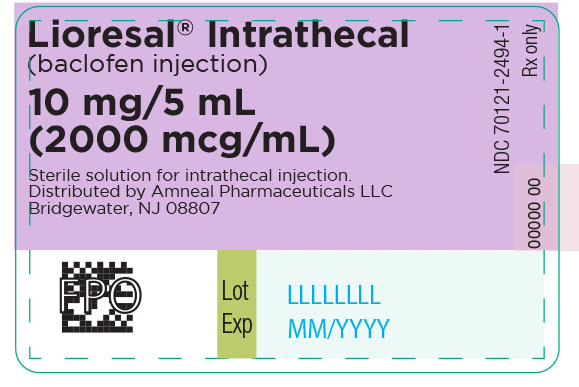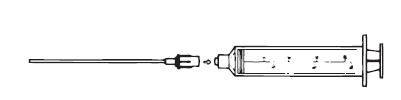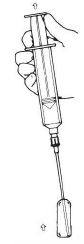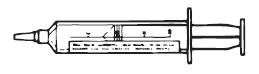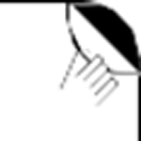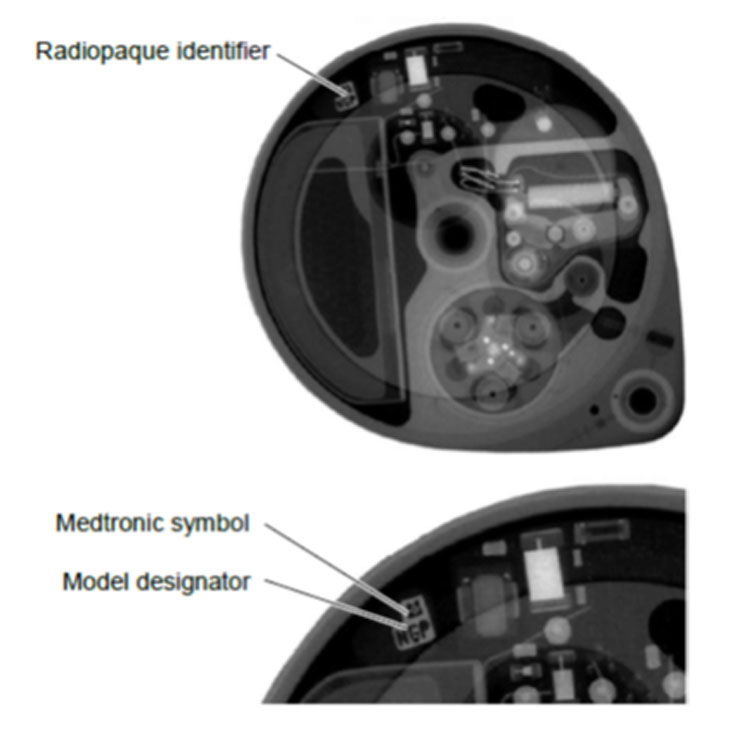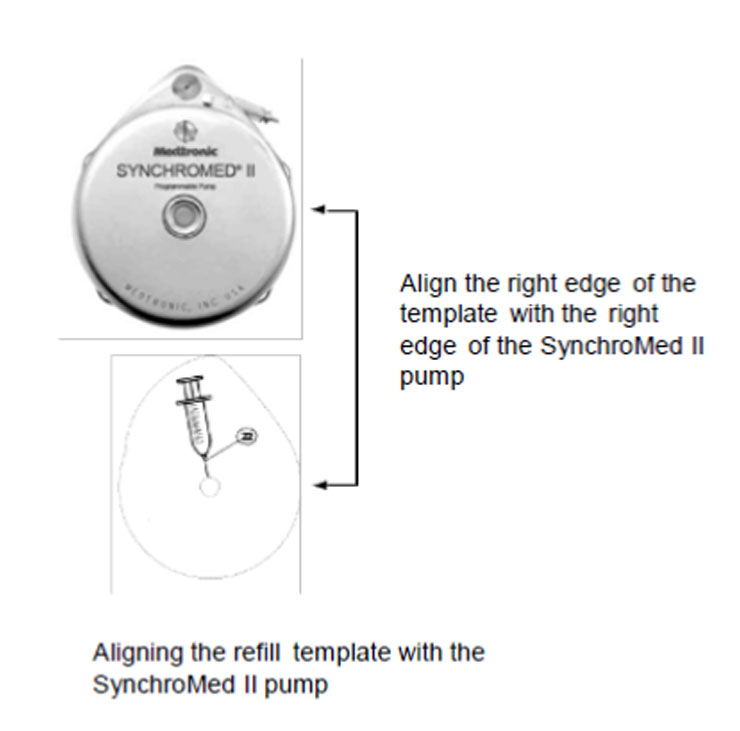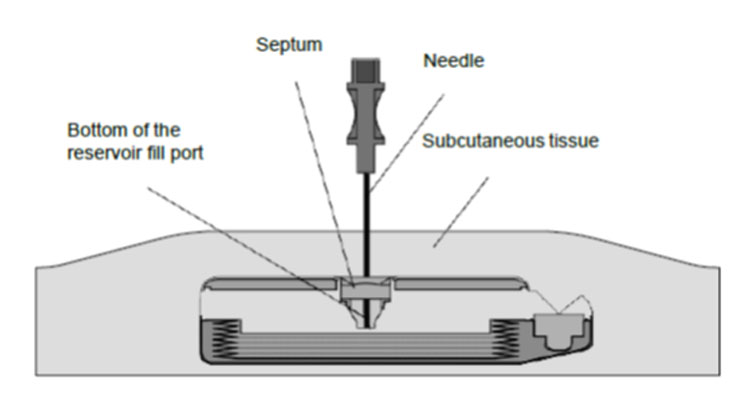 DRUG LABEL: Lioresal (baclofen)
NDC: 70121-2501 | Form: KIT | Route: INTRATHECAL
Manufacturer: Amneal Pharmaceuticals LLC
Category: prescription | Type: HUMAN PRESCRIPTION DRUG LABEL
Date: 20221209

ACTIVE INGREDIENTS: BACLOFEN 10 mg/20 mL
INACTIVE INGREDIENTS: SODIUM CHLORIDE; WATER

LIORESAL® INTRATHECAL
(baclofen injection)

BOXED WARNING

Abrupt discontinuation of intrathecal baclofen, regardless of the cause, has resulted in sequelae that include high fever, altered mental status, exaggerated rebound spasticity, and muscle rigidity, that in rare cases has advanced to rhabdomyolysis, multiple organ-system failure and death.

Prevention of abrupt discontinuation of intrathecal baclofen requires careful attention to programming and monitoring of the infusion system, refill scheduling and procedures, and pump alarms. Patients and caregivers should be advised of the importance of keeping scheduled refill visits and should be educated on the early symptoms of baclofen withdrawal. Special attention should be given to patients at apparent risk (e.g. spinal cord injuries at T-6 or above, communication difficulties, history of withdrawal symptoms from oral or intrathecal baclofen). Consult the technical manual of the implantable infusion system for additional postimplant clinician and patient information (see WARNINGS).

DESCRIPTION

LIORESAL INTRATHECAL (baclofen injection) is a muscle relaxant and antispastic. Its chemical name is 4-amino-3-(4-chlorophenyl) butanoic acid, and its structural formula is:

Baclofen is a white to off-white, odorless or practically odorless crystalline powder, with a molecular weight of 213.66. It is slightly soluble in water, very slightly soluble in methanol, and insoluble in chloroform.

LIORESAL INTRATHECAL is a sterile, pyrogen-free, isotonic solution free of antioxidants, preservatives or other potentially neurotoxic additives indicated only for intrathecal administration. The drug is stable in solution at 37° C and compatible with CSF. Each milliliter of LIORESAL INTRATHECAL contains baclofen U. S. P. 50 mcg, 500 mcg or 2000 mcg and sodium chloride 9 mg in Water for Injection; pH range is 5.0 - 7.0. Each ampule is intended for SINGLE USE ONLY. Discard any unused portion. DO NOT AUTOCLAVE.

CLINICAL PHARMACOLOGY

The precise mechanism of action of baclofen as a muscle relaxant and antispasticity agent is not fully understood. Baclofen inhibits both monosynaptic and polysynaptic reflexes at the spinal level, possibly by decreasing excitatory neurotransmitter release from primary afferent terminals, although actions at supraspinal sites may also occur and contribute to its clinical effect. Baclofen is a structural analog of the inhibitory neurotransmitter gamma-aminobutyric acid (GABA), and may exert its effects by stimulation of the GABAB receptor subtype.

LIORESAL INTRATHECAL when introduced directly into the intrathecal space permits effective CSF concentrations to be achieved with resultant plasma concentrations 100 times less than those occurring with oral administration. In people, as well as in animals, baclofen has been shown to have general CNS depressant properties as indicated by the production of sedation with tolerance, somnolence, ataxia, and respiratory and cardiovascular depression.

Pharmacodynamics of LIORESAL INTRATHECAL:

Intrathecal Bolus:

Adult Patients: The onset of action is generally one-half hour to one hour after an intrathecal bolus. Peak spasmolytic effect is seen at approximately four hours after dosing and effects may last four to eight hours. Onset, peak response, and duration of action may vary with individual patients depending on the dose and severity of symptoms.

Pediatric Patients: The onset, peak response and duration of action is similar to those seen in adult patients.

Continuous Infusion:

LIORESAL INTRATHECAL'S antispastic action is first seen at 6 to 8 hours after initiation of continuous infusion. Maximum activity is observed in 24 to 48 hours.

Continuous Infusion: No additional information is available for pediatric patients.

Pharmacokinetics of LIORESAL INTRATHECAL:

The pharmacokinetics of CSF clearance of LIORESAL INTRATHECAL calculated from intrathecal bolus or continuous infusion studies approximates CSF turnover, suggesting elimination is by bulk-flow removal of CSF.

Intrathecal Bolus: After a bolus lumbar injection of 50 or 100 mcg LIORESAL INTRATHECAL in seven patients, the average CSF elimination half-life was 1.51 hours over the first four hours and the average CSF clearance was approximately 30 mL/hour.

Continuous Infusion: The mean CSF clearance for LIORESAL INTRATHECAL (baclofen injection) was approximately 30 mL/hour in a study involving ten patients on continuous intrathecal infusion. Concurrent plasma concentrations of baclofen during intrathecal administration are expected to be low (0- 5 ng/mL).

Limited pharmacokinetic data suggest that a lumbar-cisternal concentration gradient of about 4:1 is established along the neuroaxis during baclofen infusion. This is based upon simultaneous CSF sampling via cisternal and lumbar tap in 5 patients receiving continuous baclofen infusion at the lumbar level at doses associated with therapeutic efficacy; the interpatient variability was great. The gradient was not altered by position.

Six pediatric patients (age 8-18 years) receiving continuous intrathecal baclofen infusion at doses of 77-400 mcg/day had plasma baclofen levels near or below 10 ng/mL.

INDICATIONS AND USAGE

LIORESAL INTRATHECAL (baclofen injection) is indicated for use in the management of severe spasticity. Patients should first respond to a screening dose of intrathecal baclofen prior to consideration for long term infusion via an implantable pump. For spasticity of spinal cord origin, chronic infusion of LIORESAL INTRATHECAL via an implantable pump should be reserved for patients unresponsive to oral baclofen therapy, or those who experience intolerable CNS side effects at effective doses. Patients with spasticity due to traumatic brain injury should wait at least one year after the injury before consideration of long term intrathecal baclofen therapy. LIORESAL INTRATHECAL is intended for use by the intrathecal route in single bolus test doses (via spinal catheter or lumbar puncture) and, for chronic use, only in implantable pumps approved by the FDA specifically for the administration of LIORESAL INTRATHECAL into the intrathecal space.

Spasticity of Spinal Cord Origin: Evidence supporting the efficacy of LIORESAL INTRATHECAL was obtained in randomized, controlled investigations that compared the effects of either a single intrathecal dose or a three day intrathecal infusion of LIORESAL INTRATHECAL to placebo in patients with severe spasticity and spasms due to either spinal cord trauma or multiple sclerosis. LIORESAL INTRATHECAL was superior to placebo on both principal outcome measures employed: change from baseline in the Ashworth rating of spasticity and the frequency of spasms.

Spasticity of Cerebral Origin: The efficacy of LIORESAL INTRATHECAL was investigated in three controlled clinical trials; two enrolled patients with cerebral palsy and one enrolled patients with spasticity due to previous brain injury. The first study, a randomized controlled cross-over trial of 51 patients with cerebral palsy, provided strong, statistically significant results; LIORESAL INTRATHECAL was superior to placebo in reducing spasticity as measured by the Ashworth Scale. A second cross-over study was conducted in 11 patients with spasticity arising from brain injury. Despite the small sample size, the study yielded a nearly significant test statistic (p= 0.066) and provided directionally favorable results. The last study, however, did not provide data that could be reliably analyzed.

LIORESAL INTRATHECAL therapy may be considered an alternative to destructive neurosurgical procedures. Prior to implantation of a device for chronic intrathecal infusion of LIORESAL INTRATHECAL, patients must show a response to LIORESAL INTRATHECAL in a screening trial (see Dosage and Administration).

CONTRAINDICATIONS

Hypersensitivity to baclofen. LIORESAL INTRATHECAL is not recommended for intravenous, intramuscular, subcutaneous or epidural administration.

WARNINGS

LIORESAL INTRATHECAL is for use in single bolus intrathecal injections (via a catheter placed in the lumbar intrathecal space or injection by lumbar puncture) and in implantable pumps approved by the FDA specifically for the intrathecal administration of baclofen. Because of the possibility of potentially life-threatening CNS depression, cardiovascular collapse, and/or respiratory failure, physicians must be adequately trained and educated in chronic intrathecal infusion therapy. The pump system should not be implanted until the patient’s response to bolus LIORESAL INTRATHECAL injection is adequately evaluated. Evaluation (consisting of a screening procedure: see Dosage and Administration) requires that LIORESAL INTRATHECAL be administered into the intrathecal space via a catheter or lumbar puncture. Because of the risks associated with the screening procedure and the adjustment of dosage following pump implantation, these phases must be conducted in a medically supervised and adequately equipped environment following the instructions outlined in the Dosage and Administration section. Resuscitative equipment should be available.

Following surgical implantation of the pump, particularly during the initial phases of pump use, the patient should be monitored closely until it is certain that the patient’s response to the infusion is acceptable and reasonably stable. On each occasion that the dosing rate of the pump and/or the concentration of LIORESAL INTRATHECAL (baclofen injection) in the reservoir is adjusted, close medical monitoring is required until it is certain that the patient’s response to the infusion is acceptable and reasonably stable.

It is mandatory that the patient, all patient caregivers, and the physicians responsible for the patient receive adequate information regarding the risks of this mode of treatment. All medical personnel and caregivers should be instructed in 1) the signs and symptoms of overdose, 2) procedures to be followed in the event of overdose and 3) proper home care of the pump and insertion site.

Overdose: Signs of overdose may appear suddenly or insidiously. Acute massive overdose may present as coma. Less sudden and/or less severe forms of overdose may present with signs of drowsiness, lightheadedness, dizziness, somnolence, respiratory depression, seizures, rostral progression of hypotonia and loss of consciousness progressing to coma. Should overdose appear likely, the patient should be taken immediately to a hospital for assessment and emptying of the pump reservoir. In cases reported to date, overdose has generally been related to pump malfunction, inadvertent subcutaneous injection, or dosing error. (See Drug Overdose Symptoms and Treatment.)

Extreme caution must be used when filling an FDA approved implantable pump. Such pumps should only be refilled through the reservoir refill septum. Inadvertent injection into the subcutaneous tissue can occur if the reservoir refill septum is not properly accessed. Some pumps are also equipped with a catheter access port that allows direct access to the intrathecal catheter. Direct injection into this catheter access port or inadvertent injection into the subcutaneous tissue may cause a life-threatening overdose.

Withdrawal: Abrupt withdrawal of intrathecal baclofen, regardless of the cause, has resulted in sequelae that included high fever, altered mental status, exaggerated rebound spasticity and muscle rigidity that in rare cases progressed to rhabdomyolysis, multiple organ-system failure, and death. In the first 9 years of post-marketing experience, 27 cases of withdrawal temporally related to the cessation of baclofen therapy were reported; six patients died. In most cases, symptoms of withdrawal appeared within hours to a few days following interruption of baclofen therapy. Common reasons for abrupt interruption of intrathecal baclofen therapy included malfunction of the catheter (especially disconnection), low volume in the pump reservoir, and end of pump battery life; human error may have played a causal or contributing role in some cases. Cases of intrathecal mass at the tip of the implanted catheter leading to withdrawal symptoms have also been reported, most of them involving pharmacy compounded analgesic admixtures (see PRECAUTIONS).

Prevention of abrupt discontinuation of intrathecal baclofen requires careful attention to programming and monitoring of the infusion system, refill scheduling and procedures, and pump alarms. Patients and caregivers should be advised of the importance of keeping scheduled refill visits and should be educated on the early symptoms of baclofen withdrawal.

All patients receiving intrathecal baclofen therapy are potentially at risk for withdrawal. Early symptoms of baclofen withdrawal may include return of baseline spasticity, pruritus, hypotension, and paresthesias. Priapism may develop or recur if treatment with intrathecal baclofen is interrupted. Some clinical characteristics of the advanced intrathecal baclofen withdrawal syndrome may resemble autonomic dysreflexia, infection (sepsis), malignant hyperthermia, neuroleptic-malignant syndrome, or other conditions associated with a hypermetabolic state or widespread rhabdomyolysis.

Rapid, accurate diagnosis and treatment in an emergency-room or intensive-care setting are important in order to prevent the potentially life-threatening central nervous system and systemic effects of intrathecal baclofen withdrawal. The suggested treatment for intrathecal baclofen withdrawal is the restoration of intrathecal baclofen at or near the same dosage as before therapy was interrupted.

However, if restoration of intrathecal delivery is delayed, treatment with GABA-ergic agonist drugs such as oral or enteral baclofen, or oral, enteral, or intravenous benzodiazepines may prevent potentially fatal sequelae. Oral or enteral baclofen alone should not be relied upon to halt the progression of intrathecal baclofen

withdrawal.

Seizures have been reported during overdose and with withdrawal from LIORESAL INTRATHECAL as well as in patients maintained on therapeutic doses of LIORESAL INTRATHECAL.

Fatalities:

Spasticity of Spinal Cord Origin: There were 16 deaths reported among the 576 U.S. patients treated with LIORESAL INTRATHECAL (baclofen injection) in pre- and post- marketing studies evaluated as of December 1992. Because these patients were treated under uncontrolled clinical settings, it is impossible to determine definitively what role, if any, LIORESAL INTRATHECAL played in their deaths. As a group, the patients who died were relatively young (mean age was 47 with a range from 25 to 63), but the majority suffered from severe spasticity of many years duration, were nonambulatory, had various medical complications such as pneumonia, urinary tract infections, and decubiti, and/or had received multiple concomitant medications. A case-by-case review of the clinical course of the 16 patients who died failed to reveal any unique signs, symptoms, or laboratory results that would suggest that treatment with LIORESAL INTRATHECAL caused their deaths. Two patients, however, did suffer sudden and unexpected death within 2 weeks of pump implantation and one patient died unexpectedly after screening.

One patient, a 44 year old male with MS, died in hospital on the second day following pump implantation. An autopsy demonstrated severe fibrosis of the coronary conduction system. A second patient, a 52 year old woman with MS and a history of an inferior wall myocardial infarction, was found dead in bed 12 days after pump implantation, 2 hours after having had documented normal vital signs. An autopsy revealed pulmonary congestion and bilateral pleural effusions. It is impossible to determine whether LIORESAL INTRATHECAL contributed to these deaths. The third patient underwent three baclofen screening trials. His medical history included SCI, aspiration pneumonia, septic shock, disseminated intravascular coagulopathy, severe metabolic acidosis, hepatic toxicity, and status epilepticus. Twelve days after screening (he was not implanted), he again experienced status epilepticus with subsequent significant neurological deterioration. Based upon prior instruction, extraordinary resuscitative measures were not pursued and the patient died.

Spasticity of Cerebral Origin: There were three deaths occurring among the 211 patients treated with LIORESAL INTRATHECAL in pre- marketing studies as of March 1996. These deaths were not attributed to the therapy.

Overinfusion – Delivery of more drug volume than the programmed rate (overinfusion) can result in unexpected overdose, or withdrawal caused by early emptying of the pump reservoir. Refer to the manufacturer’s pump manual and instructions for refilling the reservoir.

PRECAUTIONS

Children should be of sufficient body mass to accommodate the implantable pump for chronic infusion. Please consult pump manufacturer‘s manual for specific recommendations.

Safety and effectiveness in pediatric patients below the age of 4 have not been established.

Screening

Patients should be infection-free prior to the screening trial with LIORESAL INTRATHECAL (baclofen injection) because the presence of a systemic infection may interfere with an assessment of the patient’s response to bolus LIORESAL INTRATHECAL.

Pump Implantation

Patients should be infection-free prior to pump implantation because the presence of infection may increase the risk of surgical complications. Moreover, a systemic infection may complicate dosing.

Pump Dose Adjustment and Titration

In most patients, it will be necessary to increase the dose gradually over time to maintain effectiveness; a sudden requirement for substantial dose escalation typically indicates a catheter complication (i. e., catheter kink or dislodgement). Reservoir refilling must be performed by fully trained and qualified personnel following the directions provided by the pump manufacturer. Inadvertent injection into the subcutaneous tissue can occur if the reservoir refill septum is not properly accessed. Subcutaneous injection may result in symptoms of a systemic overdose or early depletion of the reservoir. Refill intervals should be carefully calculated to prevent depletion of the reservoir, as this would result in the return of severe spasticity and possibly symptoms of withdrawal.

Strict aseptic technique in filling is required to avoid bacterial contamination and serious infection. A period of observation appropriate to the clinical situation should follow each refill or manipulation of the drug reservoir.

Extreme caution must be used when filling an FDA approved implantable pump equipped with an injection port that allows direct access to the intrathecal catheter. Direct injection into the catheter through the catheter access port may cause a life-threatening overdose.

Additional considerations pertaining to dosage adjustment: It may be important to titrate the dose to maintain some degree of muscle tone and allow occasional spasms to: 1) help support circulatory function, 2) possibly prevent the formation of deep vein thrombosis, 3) optimize activities of daily living and ease of care.

Except in overdose related emergencies, the dose of LIORESAL INTRATHECAL should ordinarily be reduced slowly if the drug is discontinued for any reason. An attempt should be made to discontinue concomitant oral antispasticity medication to avoid possible overdose or adverse drug interactions, either prior to screening or following implant and initiation of chronic LIORESAL INTRATHECAL infusion. Reduction and discontinuation of oral anti-spasmotics should be done slowly and with careful monitoring by the physician. Abrupt reduction or discontinuation of concomitant antispastics should be avoided.

Drowsiness: Drowsiness has been reported in patients on LIORESAL INTRATHECAL. Patients should be cautioned regarding the operation of automobiles or other dangerous machinery, and activities made hazardous by decreased alertness. Patients should also be cautioned that the central nervous system depressant effects of LIORESAL INTRATHECAL (baclofen injection) may be additive to those of alcohol and other CNS depressants.

Intrathecal mass: Cases of intrathecal mass at the tip of the implanted catheter have been reported, most of them involving pharmacy compounded analgesic admixtures. The most frequent symptoms associated with intrathecal mass are: 1) decreased therapeutic response (worsening spasticity, return of spasticity when previously well controlled, withdrawal symptoms, poor response to escalating doses, or frequent or large dosage increases), 2) pain, 3) neurological deficit/dysfunction. Clinicians should monitor patients on intraspinal therapy carefully for any new neurological signs or symptoms. In patients with new neurological signs or symptoms suggestive of an intrathecal mass, consider a neurosurgical consultation, since many of the symptoms of inflammatory mass are not unlike the symptoms experienced by patients with severe spasticity from their disease. In some cases, performance of an imaging procedure may be appropriate to confirm or rule-out the diagnosis of an intrathecal mass.

Precautions in special patient populations: Careful dose titration of LIORESAL INTRATHECAL is needed when spasticity is necessary to sustain upright posture and balance in locomotion or whenever spasticity is used to obtain optimal function and care.

Patients suffering from psychotic disorders, schizophrenia, or confusional states should be treated cautiously with LIORESAL INTRATHECAL and kept under careful surveillance, because exacerbations of these conditions have been observed with oral administration.

LIORESAL INTRATHECAL should be used with caution in patients with a history of autonomic dysreflexia. The presence of nociceptive stimuli or abrupt withdrawal of LIORESAL INTRATHECAL (baclofen injection) may cause an autonomic dysreflexic episode.

Because LIORESAL is primarily excreted unchanged by the kidneys, it should be given with caution in patients with impaired renal function and it may be necessary to reduce the dosage.

LABORATORY TESTS

No specific laboratory tests are deemed essential for the management of patients on LIORESAL INTRATHECAL.

DRUG INTERACTIONS

There is inadequate systematic experience with the use of LIORESAL INTRATHECAL in combination with other medications to predict specific drug-drug interactions. Interactions attributed to the combined use of LIORESAL INTRATHECAL and epidural morphine include hypotension and dyspnea.

CARCINOGENESIS, MUTAGENESIS, AND IMPAIRMENT OF FERTILITY

No increase in tumors was seen in rats receiving baclofen orally for two years. Adequate genotoxicity assays of baclofen have not been performed.

PREGNANCY

There are no adequate and well-controlled studies in pregnant women. In animal studies, baclofen had adverse effects on embryofetal development when administered orally to pregnant rats. LIORESAL INTRATHECAL should be used during pregnancy only if the potential benefit justifies the potential risk to the fetus. Baclofen given orally increased the incidence of fetal structural abnormalities (omphaloceles) in rats. Reductions in food intake and body weight gain were observed in the dams. Fetal structural abnormalities were not observed in mice or rabbits

NURSING MOTHERS

In mothers treated with oral LIORESAL (baclofen USP) in therapeutic doses, the active substance passes into the milk. It is not known whether detectable levels of drug are present in milk of nursing mothers receiving LIORESAL INTRATHECAL. As a general rule, nursing should be undertaken while a patient is receiving LIORESAL INTRATHECAL only if the potential benefit justifies the potential risks to the infant.

PEDIATRIC USE

Children should be of sufficient body mass to accommodate the implantable pump for chronic infusion. Please consult pump manufacturer‘s manual for specific recommendations.

Safety and effectiveness in pediatric patients below the age of 4 have not been established.

Considerations based on experience with oral LIORESAL (baclofen USP)

A dose-related increase in incidence of ovarian cysts was observed in female rats treated chronically with oral LIORESAL. Ovarian cysts have been found by palpation in about 4% of the multiple sclerosis patients who were treated with oral LIORESAL for up to one year. In most cases these cysts disappeared spontaneously while patients continued to receive the drug. Ovarian cysts are estimated to occur spontaneously in approximately 1% to 5% of the normal female population.

ADVERSE REACTIONS

Spasticity of Spinal Cord Origin – Clinical Studies:

Commonly Observed in Patients with Spasticity of Spinal Origin — In pre- and post- marketing clinical trials, the most commonly observed adverse events associated with use of LIORESAL INTRATHECAL (baclofen injection) which were not seen at an equivalent incidence among placebo-treated patients were: somnolence, dizziness, nausea, hypotension, headache, convulsions and hypotonia

Associated with Discontinuation of Treatment — 8/474 patients with spasticity of spinal cord origin receiving long term infusion of LIORESAL INTRATHECAL in pre- and post- marketing clinical studies in the U. S. discontinued treatment due to adverse events. These include: pump pocket infections (3), meningitis (2), wound dehiscence (1), gynecological fibroids (1) and pump overpressurization (1) with unknown, if any, sequela. Eleven patients who developed coma secondary to overdose had their treatment temporarily suspended, but all were subsequently restarted and were not, therefore, considered to be true discontinuations.

Fatalities — See Warnings.

Incidence in Controlled Trials — Experience with LIORESAL INTRATHECAL (baclofen injection) obtained in parallel, placebo-controlled, randomized studies provides only a limited basis for estimating the incidence of adverse events because the studies were of very brief duration (up to three days of infusion) and involved only a total of 63 patients. The following events occurred among the 31 patients receiving LIORESAL INTRATHECAL (baclofen injection) in two randomized, placebo-controlled trials: hypotension (2), dizziness (2), headache (2), dyspnea (1). No adverse events were reported among the 32 patients receiving placebo in these studies.

Events Observed during the Pre- and Post-marketing Evaluation of LIORESAL INTRATHECAL — Adverse events associated with the use of LIORESAL INTRATHECAL reflect experience gained with 576 patients followed prospectively in the United States. They received LIORESAL INTRATHECAL for periods of one day (screening) (N = 576) to over eight years (maintenance) (N = 10). The usual screening bolus dose administered prior to pump implantation in these studies was typically 50 mcg. The maintenance dose ranged from 12 mcg to 2003 mcg per day. Because of the open, uncontrolled nature of the experience, a causal linkage between events observed and the administration of LIORESAL INTRATHECAL cannot be reliably assessed in many cases and many of the adverse events reported are known to occur in association with the underlying conditions being treated. Nonetheless, many of the more commonly reported reactions— hypotonia, somnolence, dizziness, paresthesia, nausea/vomiting and headache— appear clearly drug-related.

Adverse experiences reported during all U.S. studies (both controlled and uncontrolled) are shown in the following table. Eight of 474 patients who received chronic infusion via implanted pumps had adverse experiences which led to a discontinuation of long term treatment in the pre- and post-marketing studies.

INCIDENCE OF MOST FREQUENT (≥1%) ADVERSE EVENTS IN PATIENTS WITH SPASTICITY OF SPINAL ORIGIN IN PROSPECTIVELY MONITORED CLINICAL TRIALS
 | Percent of Patients Reporting Events
 | N = 576 Screening* Percent | N = 474 Titration† Percent | N = 430 Maintenance‡ Percent
Adverse Event
Hypotonia | 5.4 | 13.5 | 25.3
Somnolence | 5.7 | 5.9 | 20.9
Dizziness | 1.7 | 1.9 | 7.9
Paresthesia | 2.4 | 2.1 | 6.7
Nausea and Vomiting | 1.6 | 2.3 | 5.6
Headache | 1.6 | 2.5 | 5.1
Constipation | 0.2 | 1.5 | 5.1
Convulsion | 0.5 | 1.3 | 4.7
Urinary Retention | 0.7 | 1.7 | 1.9
Dry Mouth | 0.2 | 0.4 | 3.3
Accidental Injury | 0.0 | 0.2 | 3.5
Asthenia | 0.7 | 1.3 | 1.4
Confusion | 0.5 | 0.6 | 2.3
Death | 0.2 | 0.4 | 3.0
Pain | 0.0 | 0.6 | 3.0
Speech Disorder | 0.0 | 0.2 | 3.5
Hypotension | 1.0 | 0.2 | 1.9
Ambylopia | 0.5 | 0.2 | 2.3
Diarrhea | 0.0 | 0.8 | 2.3
Hypoventilation | 0.2 | 0.8 | 2.1
Coma | 0.0 | 1.5 | 0.9
Impotence | 0.2 | 0.4 | 1.6
Peripheral Edema | 0.0 | 0.0 | 2.3
Urinary Incontinence | 0.0 | 0.8 | 1.4
Insomnia | 0.0 | 0.4 | 1.6
Anxiety | 0.2 | 0.4 | 0.9
Depression | 0.0 | 0.0 | 1.6
Dyspnea | 0.3 | 0.0 | 1.2
Fever | 0.5 | 0.2 | 0.7
Pneumonia | 0.2 | 0.2 | 1.2
Urinary Frequency | 0.0 | 0.6 | 0.9
Urticaria | 0.2 | 0.2 | 1.2
Anorexia | 0.0 | 0.4 | 0.9
Diplopia | 0.0 | 0.4 | 0.9
Dysautonomia | 0.2 | 0.2 | 0.9
Hallucinations | 0.3 | 0.4 | 0.5
Hypertension | 0.2 | 0.6 | 0.5
N= total number of patients entering each period
%=% of patients evaluated

In addition to the more common (1% or more) adverse events reported in the prospectively followed 576 domestic patients in pre- and post-marketing studies, experience from an additional 194 patients exposed to LIORESAL INTRATHECAL (baclofen injection) from foreign studies has been reported. The following adverse events, not described in the table, and arranged in decreasing order of frequency, and classified by body system, were reported:

Nervous System: Abnormal gait, thinking abnormal, tremor, amnesia, twitching, vasodilitation, cerebrovascular accident, nystagmus, personality disorder, psychotic depression, cerebral ischemia, emotional lability, euphoria, hypertonia, ileus, drug dependence, incoordination, paranoid reaction and ptosis.

Digestive System: Flatulence, dysphagia, dyspepsia and gastroenteritis.

Cardiovascular: Postural hypotension, bradycardia, palpitations, syncope, arrhythmia ventricular, deep thrombophlebitis, pallor and tachycardia.

Respiratory: Respiratory disorder, aspiration pneumonia, hyperventilation, pulmonary embolus and rhinitis.

Urogenital: Hematuria and kidney failure.

Skin and Appendages: Alopecia and sweating.

Metabolic and Nutritional Disorders: Weight loss, albuminuria, dehydration and hyperglycemia.

Special Senses: Abnormal vision, abnormality of accommodation, photophobia, taste loss and tinnitus.

Body as a Whole: Suicide, lack of drug effect, abdominal pain, hypothermia, neck rigidity, chest pain, chills, face edema, flu syndrome and overdose.

Hemic and Lymphatic System: Anemia.

Spasticity of Cerebral Origin — Clinical Studies:

Commonly Observed — In pre-marketing clinical trials, the most commonly observed adverse events associated with use of LIORESAL INTRATHECAL (baclofen injection) which were not seen at an equivalent incidence among placebo-treated patients included: agitation, constipation, somnolence, leukocytosis, chills, urinary retention and hypotonia.

Associated with Discontinuation of Treatment — Nine of 211 patients receiving LIORESAL INTRATHECAL in pre-marketing clinical studies in the U.S. discontinued long term infusion due to adverse events associated with intrathecal therapy. The nine adverse events leading to discontinuation were: infection (3), CSF leaks (2), meningitis (2), drainage (1), and unmanageable trunk control (1).

Fatalities — Three deaths, none of which were attributed to LIORESAL INTRATHECAL, were reported in patients in clinical trials involving patients with spasticity of cerebral origin. See Warnings on other deaths reported in spinal spasticity patients.

Incidence in Controlled Trials — Experience with LIORESAL INTRATHECAL (baclofen injection) obtained in parallel, placebo-controlled, randomized studies provides only a limited basis for estimating the incidence of adverse events because the studies involved a total of 62 patients exposed to a single 50 mcg intrathecal bolus. The following events occurred among the 62 patients receiving LIORESAL INTRATHECAL in two randomized, placebo-controlled trials involving cerebral palsy and head injury patients, respectively: agitation, constipation, somnolence, leukocytosis, nausea, vomiting, nystagmus, chills, urinary retention, and hypotonia.

Events Observed during the Pre-marketing Evaluation of LIORESAL INTRATHECAL — Adverse events associated with the use of LIORESAL INTRATHECAL reflect experience gained with a total of 211 U. S. patients with spasticity of cerebral origin, of whom 112 were pediatric patients (under age 16 at enrollment). They received LIORESAL INTRATHECAL for periods of one day (screening) (N= 211) to 84 months (maintenance) (N= 1). The usual screening bolus dose administered prior to pump implantation in these studies was 50-75 mcg. The maintenance dose ranged from 22 mcg to 1400 mcg per day. Doses used in this patient population for long term infusion are generally lower than those required for patients with spasticity of spinal cord origin.

Because of the open, uncontrolled nature of the experience, a causal linkage between events observed and the administration of LIORESAL INTRATHECAL cannot be reliably assessed in many cases. Nonetheless, many of the more commonly reported reactions— somnolence, dizziness, headache, nausea, hypotension, hypotonia and coma— appear clearly drug-related.

The most frequent (≥1%) adverse events reported during all clinical trials are shown in the following table. Nine patients discontinued long term treatment due to adverse events.

INCIDENCE OF MOST FREQUENT (≥ 1%) ADVERSE EVENTS IN PATIENTS WITH SPASTICITY OF CEREBRAL ORIGIN IN PROSPECTIVELY MONITORED CLINICAL TRIALS
 | Percent of Patients Reporting Events
 | N = 211 Screening* Percent | N = 153 Titration† Percent | N = 150 Maintenance‡ Percent
Adverse Event
Hypotonia | 2.4 | 14.4 | 34.7
Somnolence | 7.6 | 10.5 | 18.7
Headache | 6.6 | 7.8 | 10.7
Nausea and Vomiting | 6.6 | 10.5 | 4.0
Vomiting | 6.2 | 8.5 | 4.0
Urinary Retention | 0.9 | 6.5 | 8.0
Convulsion | 0.9 | 3.3 | 10.0
Dizziness | 2.4 | 2.6 | 8.0
Nausea | 1.4 | 3.3 | 7.3
Hypoventilation | 1.4 | 1.3 | 4.0
Hypertonia | 0.0 | 0.7 | 6.0
Paresthesia | 1.9 | 0.7 | 3.3
Hypotension | 1.9 | 0.7 | 2.0
Increased Salivation | 0.0 | 2.6 | 2.7
Back Pain | 0.9 | 0.7 | 2.0
Constipation | 0.5 | 1.3 | 2.0
Pain | 0.0 | 0.0 | 4.0
Pruritus | 0.0 | 0.0 | 4.0
Diarrhea | 0.5 | 0.7 | 2.0
Peripheral Edema | 0.0 | 0.0 | 3.3
Thinking Abnormal | 0.5 | 1.3 | 0.7
Agitation | 0.5 | 0.0 | 1.3
Asthenia | 0.0 | 0.0 | 2.0
Chills | 0.5 | 0.0 | 1.3
Coma | 0.5 | 0.0 | 1.3
Dry Mouth | 0.5 | 0.0 | 1.3
Pneumonia | 0.0 | 0.0 | 2.0
Speech Disorder | 0.5 | 0.7 | 0.7
Tremor | 0.5 | 0.0 | 1.3
Urinary Incontinence | 0.0 | 0.0 | 2.0
Urination Impaired | 0.0 | 0.0 | 2.0
N= Total number of patients entering each period. 211 patients received drug; (1 of 212) received placebo only.

The more common (1% or more) adverse events reported in the prospectively followed 211 patients exposed to LIORESAL INTRATHECAL (baclofen injection) have been reported. In the total cohort, the following adverse events, not described in the table, and arranged in decreasing order of frequency, and classified by body

system, were reported:

Nervous System: Akathisia, ataxia, confusion, depression, opisthotonos, amnesia, anxiety, hallucinations, hysteria, insomnia, nystagmus, personality disorder, reflexes decreased, and vasodilitation.

Digestive System: Dysphagia, fecal incontinence, gastrointestinal hemorrhage and tongue disorder.

Cardiovascular: Bradycardia.

Respiratory: Apnea, dyspnea and hyperventilation.

Urogenital: Abnormal ejaculation, kidney calculus, oliguria and vaginitis.

Skin and Appendages: Rash, sweating, alopecia, contact dermatitis and skin ulcer.

Special Senses: Abnormality of accommodation.

Body as a Whole: Death, fever, abdominal pain, carcinoma, malaise and hypothermia.

Hemic and Lymphatic System: Leukocytosis and petechial rash.

Postmarketing Experience:

The following adverse events have been reported during post-approval use of LIORESAL INTRATHECAL. Because these events are reported voluntarily from a population of uncertain size, it is not possible to reliably estimate their frequency.

Musculoskeletal: The onset of scoliosis or worsening of a pre-existing scoliosis has been reported.

Urogenital: Sexual dysfunction in men and women, including decreased libido and orgasm dysfunction, have been reported. Erectile dysfunction in men has also been reported. Priapism has been reported following baclofen withdrawal.

OVERDOSAGE

Special attention must be given to recognizing the signs and symptoms of overdosage, especially during the initial screening and dose-titration phase of treatment, but also during reintroduction of LIORESAL INTRATHECAL after a period of interruption in therapy.

Symptoms of LIORESAL INTRATHECAL Overdose: Drowsiness, lightheadedness, dizziness, somnolence, respiratory depression, hypothermia, seizures, rostral progression of hypotonia and loss of consciousness progressing to coma of up to 72 hr. duration. In most cases reported, coma was reversible without sequelae after drug was discontinued. Symptoms of LIORESAL INTRATHECAL overdose were reported in a sensitive adult patient after receiving a 25 mcg intrathecal bolus.

Treatment Suggestions for Overdose:

There is no specific antidote for treating overdoses of LIORESAL INTRATHECAL (baclofen injection); however, the following steps should ordinarily be undertaken:

1) Residual LIORESAL INTRATHECAL solution should be removed from the pump as soon as possible.

2) Patients with respiratory depression should be intubated if necessary, until the drug is eliminated.

If lumbar puncture is not contraindicated, consideration should be given to withdrawing 30-40 mL of CSF to reduce CSF baclofen concentration.

DOSAGE AND ADMINISTRATION

Refer to the manufacturer's manual for the implantable pump approved for intrathecal infusion for specific instructions and precautions for programming the pump and/or refilling the reservoir. There are various pumps with varying reservoir volumes and there are various refill kits available. It is important to be familiar with all of these products in order to select the appropriate refill kit for the particular pump in use.

Screening Phase: Prior to pump implantation and initiation of chronic infusion of LIORESAL INTRATHECAL (baclofen injection), patients must demonstrate a positive clinical response to a LIORESAL INTRATHECAL bolus dose administered intrathecally in a screening trial. The screening trial employs LIORESAL INTRATHECAL at a concentration of 50 mcg/mL. A 1 mL ampule (50 mcg/mL) is available for use in the screening trial. The screening procedure is as follows. An initial bolus containing 50 micrograms in a volume of 1 milliliter is administered into the intrathecal space by barbotage over a period of not less than one minute. The patient is observed over the ensuing 4 to 8 hours. A positive response consists of a significant decrease in muscle tone and/or frequency and/or severity of spasms. If the initial response is less than desired, a second bolus injection may be administered 24 hours after the first. The second screening bolus dose consists of 75 micrograms in 1.5 milliliters. Again, the patient should be observed for an interval of 4 to 8 hours. If the response is still inadequate, a final bolus screening dose of 100 micrograms in 2 milliliters may be administered 24 hours later.

Pediatric Patients: The starting screening dose for pediatric patients is the same as in adult patients, i.e., 50 mcg. However, for very small patients, a screening dose of 25 mcg may be tried first. Patients who do not respond to a 100 mcg intrathecal bolus should not be considered candidates for an implanted pump for chronic infusion.

Post-Implant Dose Titration Period: To determine the initial total daily dose of LIORESAL INTRATHECAL following implant, the screening dose that gave a positive effect should be doubled and administered over a 24-hour period, unless the efficacy of the bolus dose was maintained for more than 8 hours, in which case the starting daily dose should be the screening dose delivered over a 24-hour period. No dose increases should be given in the first 24 hours (i.e., until the steady state is achieved).

Adult Patients with Spasticity of Spinal Cord Origin: After the first 24 hours, for adult patients, the daily dosage should be increased slowly by 10-30% increments and only once every 24 hours, until the desired clinical effect is achieved.

Adult Patients with Spasticity of Cerebral Origin: After the first 24 hours, the daily dose should be increased slowly by 5-15% only once every 24 hours, until the desired clinical effect is achieved.

Pediatric Patients: After the first 24 hours, the daily dose should be increased slowly by 5-15% only once every 24 hours, until the desired clinical effect is achieved. If there is not a substantive clinical response to increases in the daily dose, check for proper pump function and catheter patency. Patients must be monitored closely in a fully equipped and staffed environment during the screening phase and dose-titration period immediately following implant. Resuscitative equipment should be immediately available for use in case of life-threatening or intolerable side effects.

Maintenance Therapy:

Spasticity of Spinal Cord Origin Patients: The clinical goal is to maintain muscle tone as close to normal as possible, and to minimize the frequency and severity of spasms to the extent possible, without inducing intolerable side effects. Very often, the maintenance dose needs to be adjusted during the first few months of therapy while patients adjust to changes in life style due to the alleviation of spasticity. During periodic refills of the pump, the daily dose may be increased by 10-40%, but no more than 40%, to maintain adequate symptom control. The daily dose may be reduced by 10-20% if patients experience side effects. Most patients require gradual increases in dose over time to maintain optimal response during chronic therapy. A sudden large requirement for dose escalation suggests a catheter complication (i.e., catheter kink or dislodgement).

Maintenance dosage for long term continuous infusion of LIORESAL INTRATHECAL (baclofen injection) has ranged from 12 mcg/day to 2003 mcg/ day, with most patients adequately maintained on 300 micrograms to 800 micrograms per day. There is limited experience with daily doses greater than 1000 mcg/day. Determination of the optimal LIORESAL INTRATHECAL dose requires individual titration. The lowest dose with an optimal response should be used.

Spasticity of Cerebral Origin Patients: The clinical goal is to maintain muscle tone as close to normal as possible and to minimize the frequency and severity of spasms to the extent possible, without inducing intolerable side effects, or to titrate the dose to the desired degree of muscle tone for optimal functions. Very often the maintenance dose needs to be adjusted during the first few months of therapy while patients adjust to changes in life style due to the alleviation of spasticity.

During periodic refills of the pump, the daily dose may be increased by 5-20%, but no more than 20%, to maintain adequate symptom control. The daily dose may be reduced by 10-20% if patients experience side effects. Many patients require gradual increases in dose over time to maintain optimal response during chronic therapy. A sudden large requirement for dose escalation suggests a catheter complication (i.e., catheter kink or dislodgement).

Maintenance dosage for long term continuous infusion of LIORESAL INTRATHECAL (baclofen injection) has ranged from 22 mcg/ day to 1400 mcg/ day, with most patients adequately maintained on 90 micrograms to 703 micrograms per day. In clinical trials, only 3 of 150 patients required daily doses greater than 1000 mcg/ day.

Pediatric Patients: Use same dosing recommendations for patients with spasticity of cerebral origin. Pediatric patients under 12 years seemed to require a lower daily dose in clinical trials. Average daily dose for patients under 12 years was 274 mcg/ day, with a range of 24 to 1199 mcg/ day. Dosage requirement for pediatric patients over 12 years does not seem to be different from that of adult patients. Determination of the optimal LIORESAL INTRATHECAL dose requires individual titration. The lowest dose with an optimal response should be used.

Potential need for dose adjustments in chronic use: During long term treatment, approximately 5% (28/627) of patients become refractory to increasing doses. There is not sufficient experience to make firm recommendations for tolerance treatment; however, this “tolerance” has been treated on occasion, in hospital, by a “drug holiday” consisting of the gradual reduction of LIORESAL INTRATHECAL over a 2 to 4 week period and switching to alternative methods of spasticity management. After the “drug holiday,” LIORESAL INTRATHECAL may be restarted at the initial continuous infusion dose.

Stability

Parenteral drug products should be inspected for particulate matter and discoloration prior to administration, whenever solution and container permit.

Delivery Specifications

The specific concentration that should be used depends upon the total daily dose required as well as the delivery rate of the pump. LIORESAL INTRATHECAL may require dilution when used with certain implantable pumps. Please consult manufacturer’s manual for specific recommendations.

Preparation Instruction:

Screening

Use the 1 mL screening ampule only (50 mcg/mL) for bolus injection into the subarachnoid space. For a 50 mcg bolus dose, use 1 mL of the screening ampule.

Use 1.5 mL of 50 mcg/mL baclofen injection for a 75 mcg bolus dose. For the maximum screening dose of 100 mcg, use 2 mL of 50 mcg/mL baclofen injection (2 screening ampules).

Maintenance

For patients who require concentrations other than 500 mcg/mL or 2000 mcg/mL, LIORESAL INTRATHECAL must be diluted.

LIORESAL INTRATHECAL must be diluted with sterile preservative free Sodium Chloride for Injection, U.S.P.

Delivery Regimen:

LIORESAL INTRATHECAL is most often administered in a continuous infusion mode immediately following implant. For those patients implanted with programmable pumps who have achieved relatively satisfactory control on continuous infusion, further benefit may be attained using more complex schedules of LIORESAL INTRATHECAL delivery. For example, patients who have increased spasms at night may require a 20% increase in their hourly infusion rate. Changes in flow rate should be programmed to start two hours before the time of desired clinical effect.

HOW SUPPLIED

LIORESAL INTRATHECAL (baclofen injection) is packaged in single use ampules containing 0.05 mg/1 mL (50 mcg/mL), 10 mg/20 mL (500 mcg/mL), 10 mg/5 mL (2000 mcg/mL), or 40 mg/20 mL (2000 mcg/mL) supplied as follows:

Screening dose (Model 8563s): five ampules each containing 0.05 mg/1 mL (50 mcg/mL)

(NDC 70121-2496-5).

LIORESAL INTRATHECAL (baclofen injection) Refill Kits. Each refill kit includes the indicated amount of LIORESAL INTRATHECAL, a drug preparation kit, a pump refill kit with accessories that are compatible with Medtronic SynchroMed® Infusion Systems, and associated instructions.

Model 8561: one ampule containing 10 mg/20 mL (500 mcg/mL)

(NDC 70121-2501-1).

Model 8562: two ampules, each contains 10 mg/5 mL (2000 mcg/mL)

(NDC 70121-2502-2).

Model 8564: one ampule containing 40 mg/20 mL (2000 mcg/mL)

(NDC 70121-2503-1).

Model 8565: two ampules, each contains 10 mg/20 mL (500 mcg/mL)

(NDC 70121-2504-2).

Model 8566: two ampules, each contains 40 mg/20 mL (2000 mcg/mL)

(NDC 70121-2505-2).

Storage

Does not require refrigeration. Do not store above 86° F (30° C). Do not freeze. Do not heat sterilize.

Distributed by:

Amneal Pharmaceuticals LLC

Bridgewater, NJ 08807

Lioresal® is a registered trademark of Amneal

SynchroMed® is a registered trademark of Medtronic, Inc.

Rev. 08-2022-00

INSTRUCTIONS FOR USE

Drug Preparation Kit

For use with Medtronic® SynchroMed Implantable Programmable Infusion Pumps

Instructions for Use

The Lioresal® Intrathecal (baclofen injection) Drug Preparation Kit is used for kit models 8561, 8562, 8564, 8565 and 8566 to draw the drug from
the ampule(s). The appropriate ampule(s) is/are placed within the corresponding kit.

In addition, each kit contains:
-Syringe cap(s)
-Filter Straw® tube(s)
-Ampule opener(s)
-Syringe label(s)
-Plastic bag
-Four gauze pads
-20 mL syringe
-Lioresal® Intrathecal (baclofen injection)
prescribing information
-Drug Preparation Kit Instructions for Use

INDICATIONS

The Lioresal® Intrathecal (baclofen injection) Drug Preparation Kit is intended for use with Medtronic SynchroMed implantable programmable infusion pumps. It is not for use with the Medtronic MiniMed® infusion pumps.
Refer to the Lioresal® lntrathecal (baclofen injection) drug Prescribing Information for indications, contraindications, warnings, precautions, dosage and administration information, and screening procedures.

CONTRAINDICATIONS

Refer to the contraindications listed in the appropriate pump technical manual, 856X refill kit instructions for use, and drug labeling.

PRECAUTIONS

If dilution of the drug is required, refer to the drug labeling for proper diluent and procedures.

For emergency procedures, refer to the Refill Kit 856X Instructions For Use that are packaged with the refill kit.

STERILIZATION

All components of the Drug Preparation Kit are sterile. Do not resterilize. Should sterility be in question, discard and use a new kit. The outside of the ampule is sterile. If sterile technique is broken,
the contents of the ampule are still sterile.

INSTRUCTIONS FOR USE

Use sterile technique throughout the procedure to prevent contamination of the components and drug.

Note: The drug ampule is not sterile.

1. Remove the drug ampule from the box. Confirm drug ampule concentration prior to drug administration.

2. Open the ampule as follows:
Note: The entire neck of the ampule is scored. An ampule opener has been provided to ease the opening of the ampule; always exercise caution when opening a glass ampule
Note: If the ampule opener is not used, use gauze pads to hold the top of the ampule when opening.

Figure 1.

a. Hold the ampule in one hand and place opener (fins first) over the neck until it rests on the base portion of the ampule. Grasp opener with forefinger and thumb while holding the ampule base. Hold ampule upright and snap. Dispose of opener and ampule top to prevent potential contamination (Figure 1).

3. Assemble the syringe and Filter Straw® tube (Figure 2), making sure the syringe connection is snug to avoid leakage.

Figure 2. Assemble syringe and Filter Straw® tube

4.Withdraw the drug from the ampule(s) (Figure 3).

Figure 3. Withdraw drug from ampule

5.Remove the Filter Straw® tube from the syringe. Appropriately discard Filter Straw® tube.

6.Purge the air from the syringe.

7. If drug syringe is to be transferred prior to procedure a syringe cap has been provided. Attach the syringe cap, making sure the cap is snug to avoid leakage.

8. For convenience, a syringe label has been provided to capture patient's name, drug name, drug concentration, and date.

9. Peel the backing from the label and attach the label to the syringe, making sure not to cover the volume indicators on the syringe (Figure 4).

Figure 4. Syringe with cap and label

10. If the drug needs to be transported, place the syringe(s) in the plastic bag.

11. If applicable, repeat steps 1 – 10 with the second syringe, Filter Straw® tube, syringe cap, and syringe label supplied in the Model 8562, 8565 and 8566 kits.

12. Refer to the 856X refill kit Instructions for Use for pump refill instructions.

Note: Purge air from syringe prior to drug administration.

Rx Only

Medtronic® and MiniMed® are trademarks of Medtronic® and are registered in the U.S. and possibly other countries.

Lioresal® is a registered trademark of Amneal

Filter Straw® is a registered trademark of B.Braun Medical Inc.

Amneal Pharmaceuticals LLC

Bridgewater, NJ 08807

Rev. 03-2023-00

INSTRUCTIONS FOR USE

Amneal Refill Kit 856X for use with Medtronic SynchroMed® Implantable Programmable Infusion Pumps

Instructions for Use

Rx only

Explanation of symbols on product or package labeling

Refer to the appropriate product for symbols that apply.

Open here

Table of contents

Introduction 7

Package contents 7

Indications 7

Contraindications 7

Warnings 7

Precautions 11

Adverse events 12

Instructions for use 12

Sterilization 12

Preliminary procedures 12

Emptying the SynchroMed pump 13

Refilling the SynchroMed pump 16

Programming the SynchroMed pump 19

After the refill procedure 19

Reservoir rinse procedure 19

Performing a reservoir rinse 19

Technical support 20

Emergency procedures 20

Lioresal Intrathecal (baclofen injection) overdose 20

Lioresal Intrathecal (baclofen injection) underdose/withdrawal 21

Emergency procedure to empty pump reservoir 22

Special notice 23

Limited Warranty 24

Amneal MODEL 856X REFILL KIT LIMITED WARRANTY 24

Refer to the Indications, Drug Stability, and Emergency Procedures reference manual^1 for indications and related information.

Refer to the appropriate information for prescribers booklet for contraindications, warnings, precautions, adverse events summary, individualization of treatment, patient selection, use in specific populations, and component disposal.

Refer to the Lioresal Intrathecal (baclofen injection) drug labeling for indications, contraindications, warnings, precautions, dosage and administration information, and screening procedures.

^1The referenced manual is available from the Medtronic website. To view, download, print, or order the manual, go to www.medtronic.com/manual or contact your Medtronic representative.

Introduction

These instructions include only the procedure for refilling the pump reservoir with Lioresal Intrathecal (baclofen injection). Refer to the appropriate technical manuals, provided by the manufacturer for instructions on implanting and/or programming of the pump.

Package contents

The Model 856X Refill Kit contains the following sterile components that are not made with natural rubber latex:

- Two 22-gauge noncoring needles
- Extension set with a clamp
- 0.2-micron filter
- 20-mL syringe
- Template
- Fenestrated drape with adhesive strips
- Accessories (adhesive bandage, sharps plug, four gauze pads, two alcohol wipes, gloves, povidone iodine swab sticks)
- Refill Kit Instructions for Use
- Sterile drape

Indications

The Model 856X Refill Kit is intended for use in refilling Medtronic SynchroMed implantable programmable infusion pumps. It is not for use with the Medtronic MiniMed infusion pumps.

Contraindications

Amneal refill kits are contraindicated for all catheter access port procedures.

Warnings

Withdrawal - Abrupt discontinuation of intrathecal baclofen, regardless of the cause, has resulted in sequelae that include high fever, altered mental status, exaggerated rebound spasticity, and muscle rigidity, that in rare cases has advanced to rhabdomyolysis, multiple organ-system failure and death.

Prevention of abrupt discontinuation of intrathecal baclofen requires careful attention to programming and monitoring of the infusion system, refill scheduling and procedures, and pump alarms. Patients and caregivers should be advised of the importance of keeping scheduled refill visits and should be educated on the early symptoms of baclofen withdrawal. Special attention should be given to patients at apparent risk (e.g. spinal cord injuries at T-6 or above, communication difficulties, history of withdrawal symptoms from oral or intrathecal baclofen). Consult the technical manual of the implantable infusion system for additional postimplant clinician and patient information.

User instructions - Comply with all product instructions for initial preparation and filling, implantation, programming, refilling, and accessing the catheter access port (if present) of the pump. Failure to comply with all instructions can lead to technical errors or improper use of implanted infusion pumps and result in additional surgical procedures, a return of underlying symptoms, drug withdrawal symptoms, or a clinically significant or fatal drug underdose or overdose.

Implantation and system management - Implantation and ongoing system management must be performed by individuals trained in the operation and handling of the infusion system and must be in compliance with procedures described in the appropriate technical instructions. Inadequate training or failure to follow instructions can require surgical revision or replacement, and result in a clinically significant or fatal drug underdose or overdose.

Overinfusion – Overinfusion is defined as the delivery of more drug volume than the programmed rate, exceeding the pump’s flow rate accuracy specification. Pump reservoir contents aspirated during a refill procedure that are less than expected may indicate that the pump has overinfused.

Overinfusion may or may not be associated with clinically relevant symptoms. When the pump delivers more drug volume than the programmed rate, patients may experience overdose symptoms, and the pump reservoir will deplete more quickly than expected. Patients may experience underdose or withdrawal symptoms if the drug is depleted prior to the scheduled refill date from an overinfusing pump. At each refill visit, question and examine the patient for signs and symptoms of overdose, underdose, and withdrawal.

The low reservoir alarm of an overinfusing pump will not sound if the pump reservoir is prematurely depleted. The low reservoir alarm is calculated from the pump’s programmed delivery rate and is not a direct measurement of the actual drug volume in the pump reservoir. Multiple factors may increase the likelihood of overinfusion, including: nonindicated drug formulations, overfilling of the pump reservoir, operation of the pump with no fluid in the reservoir, catheter occlusion, and pump stops or motor stalls lasting more than 48 hours.

Refer to the appropriate drug labeling for specific drug underdose or overdose symptoms and methods of management. If overinfusion is strongly suspected, contact Medtronic. Reducing the dose and/or concentration is not recommended as a solution for overinfusion. If immediate discontinuation of therapy is clinically appropriate for the patient, program the pump to minimum rate mode, and aspirate any remaining drug from the reservoir. Five occurrences of overinfusion have been identified in Medtronic’s prospective, long-term multi-center registry study (Product Surveillance Registry) as of January 2016, resulting in a rate estimate of less than 0.14% (approximately 1 in 700).

Calculating catheter volume - Use the catheter length recorded at implant or catheter revision when calculating catheter volume. The actual implanted catheter length and catheter model number are required to accurately calculate catheter volume. A universal value does not exist that can be used as a substitute for this knowledge. An inaccurate catheter volume calculation can result in a clinically significant or fatal drug underdose or overdose.

Contrast medium (pumps with a catheter access port) - Do not inject any contrast medium into the pump reservoir. Injecting contrast medium into the pump reservoir can impair pump operation.

Refill - Patients must return to the clinic for refills at the prescribed times. Failure to return to the clinic for refills at the prescribed times can result in the actual flow rate of the pump being less than expected, resulting in a loss of or change in therapy, which may lead to a return of underlying symptoms, drug withdrawal symptoms, or a clinically significant or fatal drug underdose. Failure to return at the prescribed times can also damage the pump, requiring surgical replacement.

Refill kit components - Use the appropriate Amneal refill kit during all Lioresal refill procedures using Medtronic implantable infusion pumps. Using components other than Amneal components or a kit other than the appropriate refill kit can damage Medtronic pump components, requiring surgical revision or replacement, and allow drug leakage into surrounding tissue, resulting in loss of or change in therapy, which may lead to a return of underlying symptoms, drug withdrawal symptoms, or a clinically significant or fatal drug underdose or overdose.

Injection error during a pump refill procedure - Be certain you are accessing the reservoir fill port when injecting fluids into an implanted pump. ALWAYS:

- identify the pump model and reservoir volume.
- identify the location of the reservoir fill port.

– Avoid pocket fill, ie, improper injection of medication into the subcutaneous tissue (see below).

– Avoid inadvertent injection into the catheter access port (see below).

- use the instructions, noncoring needles, appropriate template edge, and other accessories provided in the appropriate kit.
- verify the location of the reservoir fill port during needle insertion according to the instructions provided AND using other medical procedures as appropriate.
- refer to the drug labeling for indications, contraindications, warnings, precautions, adverse events, and dosage and administration information.

Pocket fill is the improper injection of refill medication into the subcutaneous tissue, which includes the pump pocket. The injection of drug into the subcutaneous tissue can lead to an acute systemic overdose, which can be fatal. After a pocket fill, the pump reservoir will become empty sooner than anticipated, and this may cause underdose symptoms and/or baclofen withdrawal syndrome, which can be fatal. If it is suspected or known that all or part of the drug was injected into the pocket during the refill procedure, monitor the patient closely for signs and symptoms of overdose in an appropriate facility for a sufficient amount of time or until the symptoms have resolved. Refer to the refill kit manual or the Indications, Drug Stability, and Emergency Procedures reference manual1 for emergency procedures associated with drug underdose and overdose. Refer to the drug product information label for specific drug underdose and overdose symptoms and methods of management.

Inadvertent injection into the catheter access port may result in a clinically significant or fatal drug overdose. If it is suspected or known that all or part of the drug was injected into the catheter access port during the refill procedure, monitor the patient closely for signs and symptoms of overdose in an appropriate facility for a sufficient amount of time or until the symptoms have resolved. Refer to the catheter access port kit manual or the Indications, Drug Stability, and Emergency Procedures reference manual1 for emergency procedures associated with drug overdose. Refer to the drug labeling for specific drug overdose symptoms and methods of management.

Changing drug or decreasing drug concentrations - Rinse the reservoir twice between solutions when changing drug or decreasing drug concentrations in the pump reservoir. A significant amount of drug may be present in the pump reservoir after emptying the pump. This residual volume cannot be removed by emptying the pump. Rinsing the reservoir between solutions minimizes the amount of drug in this residual volume but does not eliminate it. Failure to account for residual drug in the pump reservoir can result in a concentration that is different than intended and a clinically significant or fatal drug underdose or overdose. Program a bridge bolus after rinsing the reservoir twice.The bridge bolus advances the remaining old drug (the drug left in the pump tubing, catheter access port, and catheter after emptying and refilling the pump) to the catheter tip at the specified flow rate.

Refer to "Performing a reservoir rinse" on page 18 of this manual. Refer to the programming guide for bridge bolus procedures.

Connections - Firmly secure all connections. Failure to secure connections can allow drug to leak onto the surrounding skin and may result in inadequate therapy or infection.

Reservoir fill port injections - Do not use excessive force when accessing the reservoir fill port. Excessive force can result in damage to the needle or pump requiring surgical revision or replacement, and leakage into surrounding tissue, resulting in loss of or change in therapy, which may lead to a return of underlying symptoms, drug withdrawal symptoms, or a clinically significant or fatal drug underdose or overdose.

Intrathecal therapy - For intrathecal therapy, use ONLY a preservative-free sterile solution indicated for intrathecal use. Nonindicated fluids containing preservatives or endotoxins can be neurotoxic in intrathecal applications. Using nonindicated fluids can result in adverse events including, but not limited to, extreme pain, cramps, seizures, and death.

Drug information - Refer to the drug labeling for indications, contraindications, warnings, precautions, dosage and administration information, and screening procedures. Refer to the drug labeling for specific drug underdose or overdose symptoms and methods of management. Failure to refer to the drug labeling can result in inappropriate patient selection and management, inadequate therapy, intolerable side effects, or a clinically significant or fatal drug underdose or overdose. Consider the possibility of a drug error if the patient experiences unusual side effects. Failure to do so can result in misdiagnosis of patient symptoms.

Mixing drugs - The effects that drug mixtures have on pump operation are unknown. Drugs can precipitate when mixed. These precipitates can inhibit pump flow or block the catheter, resulting in loss of therapy or a clinically significant or fatal drug underdose.

Drug interaction and side effects - Inform patients of the appropriate warnings and precautions regarding drug interactions, potential side effects, and signs and symptoms that require medical attention, including prodromal signs and symptoms of inflammatory mass. Failure to recognize the signs and symptoms and to seek appropriate medical intervention can result in serious patient injury or death.

Drug overdose symptoms and management - Refer to the emergency procedures included at the end of this manual and the drug labeling for specific drug overdose symptoms and methods of management.

Drug underdose/overdose - Inform patients and caregivers of the signs and symptoms of a drug underdose and overdose. Inform patients and caregivers:

- to be aware and report any unusual signs or symptoms at anytime during or after a refill or catheter access port procedure.
- to be alert for any burning sensations in the area of the pump pocket during their refill or catheter access port procedure.
- to especially watch for signs of underdose and overdose.
- to stay alert for signs or symptoms that may indicate changes to their prescribed drug concentration or programmed dose.
- to seek emergency assistance as necessary. Refer to the refill kit or catheter access port kit manual or the Indications, Drug Stability and Emergency Procedures reference manual1 for emergency procedures associated with drug underdose and overdose.

Failure to recognize these signs and symptoms and to seek appropriate medical intervention can result in serious patient injury or death.

Patient travel – Patients should notify their clinicians of any travel plans. Clinicians need this information to coordinate patient care and pump refills and help prevent a loss of or change in therapy, which may lead to a return of underlying symptoms, drug withdrawal symptoms, or a clinically significant or fatal drug underdose.

Precautions

Compatibility, all components - Follow these guidelines when selecting system components:

- Amnealcomponents: For proper therapy, use only components that are compatible with the appropriate indication.
- Non-Amneal components: No claims of safety, efficacy, or compatibility are made with regard to the use of non-Amneal components. Refer to the non-Amneal component documentation for information.

Component packaging - Before shipment the components in the sterile package were sterilized by the process indicated on the package label. Do not use or implant a component if the following circumstances have occurred:

- The storage package or sterile seal has been pierced or altered because component sterility cannot be guaranteed and infection may occur.
- The component shows signs of damage because the component may not function properly.
- The use-by date has expired because component sterility cannot be guaranteed and infection may occur; also, device battery longevity may be reduced and may require early replacement.

Storage temperature: kits and accessories - Do not store or transport the kit device components or accessories above 57 °C (135 °F) or below –34 °C (–30 °F). Temperatures outside this range can damage device components.

Aseptic technique - Use strict aseptic technique when accessing the reservoir fill port or the catheter access port of an implanted pump. Failure to use aseptic technique can contaminate fluids or tissues and result in local or systemic infection.

Infection - Use extreme caution when accessing the reservoir fill port or catheter access port of the implanted pump if local or systemic infection is suspected. Avoid contaminating the system or further spreading the infection. Local or systemic infection may require pump revision or removal.

Therapy discontinuance - If therapy is discontinued for an extended period, fill the pump reservoir with preservative-free saline. Program the pump to infuse at the minimum flow rate. Refill the pump as needed to ensure the pump always contains fluid in the reservoir and fluid pathway. Stopping the pump for extended periods or allowing the pump reservoir to empty completely can damage the system and require surgical replacement.

Single use only - Do not reuse any component. Components are intended for single use only. Reusing components can result in inadequate therapy and an increased risk of infection.

Reservoir valve activation - Do not prematurely activate the pump reservoir valve. Activation of the pump reservoir valve seals the pump reservoir valve closed. Unusual resistance or the inability to inject the entire fill volume may indicate activation of the pump reservoir valve. If the valve closes, a portion of the reservoir contents must be delivered or removed before filling can be completed, and procedural delays can occur. Activation of the pump reservoir valve before the pump is filled can be resolved by the following actions:

- completely aspirating all contents of the pump reservoir before filling
- not allowing air into the pump reservoir through an open needle in the septum or an unclamped extension
- not exceeding the maximum reservoir volume indicated in the pump labeling
- If the patient has a fever, waiting for the patient’s fever to reduce to 38°C or below

Adverse events

The adverse events associated with the use of this device may include, but may not be limited to, the following:

- Meningitis
- Infection
- Reservoir contamination
- Overpressurization of the reservoir
- Injection into pocket or subcutaneous tissue
- Activation of reservoir valve

Instructions for use

Become thoroughly familiar with all product literature before using this refill kit.

Sterilization

All components of the kit are sterile. Do not resterilize. Should sterility of the kit be in question, discard and use a new kit.

Note: The outside of the ampule is sterile. If sterile technique is broken, the contents of the ampule are still sterile.

Preliminary procedures

1. Open the Lioresal Refill Kit
2. Prepare the sterile field. The sterile drape can be used to prepare the sterile field.
3. Gather the following sterile equipment:

- Drug prep kit containing correct concentration and volume of Lioresal Intrathecal (baclofen injections)
- Sterile drape

From the refill kit:

- 20-mL empty syringe
- Extension set with a clamp
- Template
- 0.2-micron filter
- Two 22-gauge noncoring needle (2", 1.5")
- Fenestrated drape with adhesive strips
- Two alcohol wipes
- Latex-free sterile gloves
- Adhesive bandage, optional
- *Note: the sharps plug should remain in the kit tray to receive the used sharps, if desired

4. Refer to the drug labeling for indications, contraindications, warnings, precautions, dosage and administration information, and screening procedures.

5. Prepare the programmer for use. Refer to the appropriate programming guide for instructions.

6. Confirm the:

- pump model
- reservoir volume (i.e., expected volume)
- location of the pump

Note: The model and reservoir volume can be confirmed by the programmer. Alternatively, a radiopaque identifier in the pump shows the pump model and identifies Medtronic as the pump manufacturer on a standard x-ray (Figure 1). A three-letter code designates the pump model.

Figure 1. A radiopaque identifier on a SynchroMed II pump.

5. Confirm that the volume of the prescribed fluid does not exceed the reservoir volume of the pump.

Emptying the SynchroMed pump

1. Prepare the injection site by cleansing the area.
2. Open the kit. Put on sterile gloves.
3. Place the drape, exposing the pump site.
4. Using sterile procedures, assemble the needle, extension set, and empty syringe as follows:

a. Connect the empty syringe to the extension set.

b. Connect the needle to the extension set.

5. Palpate the pump and identify the location of the catheter access port and the edges of pump.

Factors that may make it difficult to locate the pump include, but are not limited to:

- deep implant
- patient position (eg, a seated patient)
- scar tissue at the pump implant site
- seroma
- the pump is tilted in the pocket
- ·obesity
- pump movement within the pocket
- weight gain after implant
- weight loss after implant

If you have difficulty identifying the pump features, you may seek assistance from another clinician. If deemed necessary by the clinician, x-ray and fluoroscopy can be used to assist in locating or determining the orientation of the pump.

6. Place the template on the skin over the pump, and align the refill template. Align the right edge of the template with the right edge of the pump (Figure 2). Use the center circle of the template to insert the needle into the reservoir fill port.

Figure 2. Aligning the refill template.

7. Close the clamp.

8. Gently insert the 22-gauge needle perpendicular to the surface of the pump through the center of the template and into the center of the reservoir fill port until the needle touches the bottom of the reservoir fill port (Figures: 3 – 4).

Note: The pump may be tilted within the pocket and therefore the needle angle may not be perpendicular to the patient's body.

During proper needle insertion, you will feel the needle:

- pass through the patient's skin and subcutaneous tissue,
- hit the silicone septum,

(Scar tissue, if present, can feel similar to the septum.)

- pass through the septum, and
- hit the metal bottom of the reservoir fill port.

(The top of the pump is metal and hitting the top of the pump can feel similar to hitting the bottom of the reservoir fill port.)

If excessive resistance is encountered during needle insertion, reassess placement. Do not force the needle. The feel of abnormal resistance during the procedure may be an indication that the needle is not in the center of the reservoir fill port.

Figure 3. View inside of a SynchroMed programmable pump while the needle is fully and properly inserted.

Figure 4. Close the clamp and insert the needle into the reservoir fill port.

Note: At any point during the procedure, if in doubt about the needle location, reassess its position. Factors that may contribute to difficulty inserting the needle into the reservoir fill port include, but are not limited to:

- the pump is flipped in the pocket
- deep implant
- patient position (eg, a seated patient)
- patient movement (eg, spasticity, difficulty hold still)
- localized muscle spasms at the pump implant site
- scar tissue at the pump implant site
- seroma
- the pump is tilted in the pocket
- obesity
- pump movement within the pocket
- weight gain after implant
- weight loss after implant

9. Open the clamp and slowly withdraw the fluid from the reservoir into the empty syringe.

Note: If the withdrawn fluid has an unexpected appearance (eg, evidence of blood), this may indicate that the needle is not properly inserted into the pump.

10. If the syringe maximum capacity is reached before the reservoir is completely empty, more than one syringe will be needed to empty the pump.

a. Close the clamp.

b. Remove the full syringe.

c. Attach an empty syringe.

d. Verify that the needle is in the pump reservoir fill port.

e. Repeat step 9, then continue to step 11.

11. Completely empty the pump. When the pump is empty, the bubbles will stop forming, and negative pressure in the syringe can be felt.

12. Close the clamp and remove the syringe from the extension set.
Note: Keep the needle in the reservoir fill port and the clamp closed for the pump refill procedure that follows.

13. Note the amount withdrawn from the pump for entry in the patient's record.

14. Compare the amount withdrawn from the pump to the expected volume. See the pump programmer for the expected volume. The amount withdrawn should approximately equal the expected volume. If a less than expected volume is observed, potential causes of the volume discrepancy could include: inaccurate volume measurements, incomplete pump aspiration, incorrect volume entry into clinician programmer at refills, unrecognized partial pocket fill, aspiration of pump medication by patient or caregiver, or overinfusion.

Note: Immediately following the refill procedure:

− record the amount withdrawn and the expected volume in the patient’s record

− record any volume discrepancy and compare volume discrepancies from visit to visit.

15. Discard the fluid and syringe as appropriate for the fluid content in accordance with institutional policies and applicable regulations.

Refilling the SynchroMed pump

WARNING:

Overinfusion is defined as the delivery of more drug volume than the programmed rate, exceeding the pump’s flow rate accuracy specification. Pump reservoir contents aspirated during a refill procedure that are less than expected may indicate that the pump has overinfused. Overinfusion may or may not be associated with clinically relevant symptoms. When the pump delivers more drug volume than the programmed rate, patients may experience overdose symptoms, and the pump reservoir will deplete more quickly than expected. Patients may experience underdose or withdrawal symptoms if the drug is depleted prior to the scheduled refill date from an overinfusing pump. At each refill visit, question and examine the patient for signs and symptoms of overdose, underdose, and withdrawal.

The low reservoir alarm of an overinfusing pump will not sound if the pump reservoir is prematurely depleted. The low reservoir alarm is calculated from the pump’s programmed delivery rate and is not a direct measurement of the actual drug volume in the pump reservoir. Multiple factors may increase the likelihood of overinfusion, including: nonindicated drug formulations, overfilling of the pump reservoir, operation of the pump with no fluid in the reservoir, catheter occlusion, and pump stops or motor stalls lasting more than 48 hours.

Refer to the appropriate drug labeling for specific drug underdose or overdose symptoms and methods of management. If overinfusion is strongly suspected, contact Medtronic. Reducing the dose and/or concentration is not recommended as a solution for overinfusion. If immediate discontinuation of therapy is clinically appropriate for the patient, program the pump to minimum rate mode, and aspirate any remaining drug from the reservoir. Five occurrences of overinfusion have been identified in Medtronic’s prospective, long-term multi-center registry study (Product Surveillance Registry) as of January 2016, resulting in a rate estimate of less than 0.14% (approximately 1 in 700).

WARNING:

Pocket fill is the improper injection into the subcutaneous tissue, which includes the pump pocket. Pocket fill can result in a loss of or change in symptom control, drug withdrawal symptoms, or a clinically significant or fatal drug underdose or overdose. Observe the patient after the pump refill procedure for any signs or symptoms that could indicate a pocket fill or any other drug-related adverse event due to the refill procedure.

Inadvertent injection into the catheter access port may result in a clinically significant or fatal drug overdose. Observe the patient after the pump refill procedure for any signs or symptoms that could indicate a drug-related adverse event due to the pump refill procedure.

WARNING:

If it is suspected or known that all or part of the drug was inadvertently injected into the pocket or the catheter access port during the refill procedure, monitor the patient closely for signs and symptoms of overdose in an appropriate facility for a sufficient amount of time or until the symptoms have resolved. Refer to the kit manual or the Indications, Drug Stability, and Emergency Procedures reference manual1 for emergency procedures associated with drug underdose and overdose. Refer to the drug product information label for specific drug underdose and overdose symptoms and methods of management.

WARNING:

Swelling at the injection site may indicate that the needle tip is not properly located within the pump reservoir, and the result could be pocket fill. Pocket fill can result in a loss of or change in symptom control, drug withdrawal symptoms, or a clinically significant or fatal drug underdose or overdose. Absence of swelling does not in all cases demonstrate that the needle tip is properly located. If swelling is present, stop injecting and observe the patient for any signs or symptoms that could indicate a pocket fill or any other drug-related adverse event.

1. If changing drug or drug concentrations, refer to "Performing a reservoir rinse" on page 18. Otherwise, proceed to the next step.
2. Confirm that the refill volume of the prescribed fluid does not exceed the reservoir volume of the pump.
3. Purge the air from the syringe containing the prescribed fluid.
4. Attach the filter to the syringe with the prescribed fluid.
5. Purge all air from the filter.
6. Attach the syringe with the prescribed fluid and filter to the extension set (Figure 5).
7. Before and during injection, verify that the needle remains fully inserted to the bottom of the reservoir fill port. Do not apply tension to the extension tubing because the needle may be pulled out from the reservoir.
8. Open the clamp and as the clamp is opened, observe the following indications that the needle continues to be properly positioned:
  - The bubbles in the extension set are immediately drawn into the pump.
  - The plunger may move slightly when the drug is initially drawn into the pump.
9. Slowly depress the plunger on the syringe to inject the prescribed fluid into the pump reservoir. While injecting the prescribed fluid, verify that the needle remains properly located within the reservoir (Figure 5).

a. Periodically withdraw and observe a portion of the drug to confirm that the drug has the expected appearance.

b. After confirming that the needle remains in the reservoir, resume injecting fluid.

Figure 5. Open the clamp and inject into the pump reservoir.

CAUTION:

If you encounter unusual resistance before the maximum reservoir volume is injected or you are unable to inject fluid, the reservoir valve may have been activated. Activation of the pump reservoir valve seals the pump reservoir valve closed. If the valve closes, a portion of the reservoir contents must be delivered or removed before filling can be completed, and procedural delays can occur.

To prevent activation of the pump reservoir valve during emptying and filling procedures:

- completely aspirate all contents of the pump reservoir before filling;
- do not allow air into the pump reservoir through an open needle in the septum or an unclamped extension; and
- do not exceed the maximum reservoir volume indicated in the pump labeling.

10. If you have activated the reservoir valve, complete steps a – g below. Otherwise, proceed to step 11.

a. Discontinue injection.

b. Close the clamp.

c. Remove the syringe with prescribed fluid and attached filter.

d. Attach an empty 20-mL syringe to the extension set.

e. Open the clamp, and aspirate until all fluid/air is removed.

f. Close the clamp and remove the syringe containing the aspirate from the extension set and discard the syringe.

g. Repeat steps 2 – 10.

Note: For pumps with a reservoir valve, the amount of time before the valve will release is dependent on the duration and the amount of pressure applied after the valve is first activated. The more pressure exerted, the longer it may take to release the valve.

11. If more than one syringe of prescribed fluid is needed to fill the pump reservoir, complete steps a – d below. Otherwise, proceed to step 12.

a. Close the clamp.

b. Keep the filter from the extension set in place, and remove the first syringe from the filter.

CAUTION: Do not remove the filter from the extension set. Removal of the filter could compromise the sterile barrier, which could result in an infection for the patient.

c. Purge the air from the second syringe, and attach the second syringe to the filter (Figure 5).

d. With the second syringe in a vertical position, open the clamp and slowly depress the plunger on the syringe to inject the prescribed fluid into the pump reservoir.

12. When filling is complete, close the clamp and carefully remove the needle from the reservoir fill port.

Note: If you are unsure whether drug was injected correctly into the pump, completely aspirate the pump to verify that all of the injected drug can be removed.

13. Remove the cleansing agent from the patient’s skin using an alcohol pad.

14. Apply an adhesive bandage, if desired.

15. Discard all components of the kit.

Programming the SynchroMed pump

1. If the drug concentration or drug has been changed, program a bridge bolus. Refer to the programming guide for the pump software.
2. If any prescription information has changed, enter the changed information into the clinician programmer: for example drug name, drug concentration, infusion information, or volume of prescribed fluid in the pump reservoir.
3. Update the pump.

After the refill procedure

1. Record the amount withdrawn and the expected volume in the patient’s record.
2. Record any volume discrepancy and compare volume discrepancies from visit to visit.
3. Print out the desired refill-related reports, and place the final pump settings in the patient file.
4. Determine the refill date from the printout, and schedule a refill appointment

Reservoir rinse procedure

Performing a reservoir rinse

To prevent drug overdose or underdose when changing concentrations or changing solutions in the pump reservoir, always rinse the reservoir twice between solutions to remove the drug that remains in the reservoir after emptying the pump. This remaining volume is known as the residual volume.

The procedure for performing a reservoir rinse is outlined below. Use the components of the appropriate refill kit to perform the rinse and follow the applicable empty and refill procedures for that kit.

1. Empty the pump completely.
2. Fill the pump with 10 mL of sterile preservative-free Sodium Chloride Injection, USP.
3. Empty the pump completely.
4. Repeat steps 2 and 3.
5. Fill the pump to capacity with the prescribed fluid.
6. Program a bridge bolus. Refer to the programming guide for the pump software.

Technical support

A toll-free technical support service is available 24 hours a day for clinicians managing patients with Medtronic implantable infusion pumps. Telephone Customer Service at: 1-800-707-0933.

Emergency procedures

Lioresal Intrathecal (baclofen injection) overdose

Consult the patient's medical record or with the patient's physician to confirm the drug or drug concentration within the pump reservoir.

Symptoms

Drowsiness, lightheadedness, dizziness, somnolence, respiratory depression, hypothermia, seizures, rostral progression of hypotonia, and loss of consciousness progressing to coma.

There is no specific antidote for treating overdoses of intrathecal baclofen injection.

Actions

See Table 1.

Table 1. Lioresal Intrathecal (baclofen injection) overdose emergency procedures

Maintain airway/breathing/circulation.
Intubation and respiratory support may be necessary.
↓
Empty pump reservoir to stop drug flow.
Record amount withdrawn.
↓ ↓ ↓
If not contraindicated, withdraw 30 – 40 mL CSF by lumbar puncture or through the catheter access port to reduce the concentration of baclofen in the CSF. Use only a 24-gauge or smaller, 1.5- or 2.0-inch (3.8- or 5.1-cm), needle for withdrawal from the catheter access port.a | Proceed immediately to the next step.
↓ | ↓
Notify patient's physician managing intrathecal baclofen injection therapy.
↓
Continue to monitor closely for symptom recurrence.
↓
Report incident to Amneal

a Use a 24- or 25-gauge needle for withdrawal from a SynchroMed II catheter access port.

Lioresal Intrathecal (baclofen injection) underdose/ withdrawal

Consult the patient's medical record or with the patient's physician to confirm the drug or drug concentration within the pump reservoir.

Symptoms of underdose

Pruritus without rash, hypotension, paresthesia, fever, and altered mental state. Priapism may develop or recur if treatment with intrathecal baclofen is interrupted.

Symptoms of withdrawal

Exaggerated rebound spasticity and muscle rigidity, rhabdomyolysis, and multiple organ failure. The condition may resemble autonomic dysreflexia, infection (sepsis), malignant hyperthermia, and neuroleptic- malignant syndrome.

Actions

See Table 2.

Table 2. Lioresal Intrathecal (baclofen injection) underdose/withdrawal emergency procedures

Initiate life-sustaining measures if indicated.

↓

If a patient receiving intrathecal baclofen injection presents with the signs and symptoms suggestive of withdrawal, the following is consistent with that suggested by a panel of therapy-experienced clinicians convened to explore this issue. a,b

1. Immediately contact a physician experienced in intrathecal baclofen injection, preferably the physician managing the therapy for the patient in question; follow the recommendations of this physician. This step is important even if the patient’s signs and symptoms seem mild.
2. If a physician experienced in intrathecal baclofen injection is unavailable, consider instituting one or more of the following options, unless otherwise contraindicated:

- high-dose oral* or enteral baclofen
- restoration of intrathecal baclofen injection infusion
- intravenous benzodiazepines by continuous or intermittent infusion, titrating the dosage until the desired therapeutic effect is achieved

* Note: Oral baclofen should not be relied upon as the sole treatment for intrathecal baclofen injection withdrawal syndrome.

↓

Report incident to Amneal

a Refer to the drug manufacturer’s package insert for a complete list of indications, contraindications, warnings, precautions, adverse events, and dosage and administration information.

b Coffey RJ, Edgar TS, Francisco GE, et al. Abrupt withdrawal from the

intrathecal baclofen: recognition and management of a potentially life- threatening syndrome. Arch Phys Med Rehabil. 2002;83:735-741.

Emergency procedure to empty pump reservoir

Equipment

- 22-gauge noncoring needle
- 20-mL syringe
- 3-way stopcock or extension set with clamp
- Antiseptic agent

1. Assemble the needle, syringe, and stopcock or extension set.
2. Locate the pump by palpation. The reservoir fill port is located in the CENTER of the pump.

If you have difficulty identifying the pump features, you may seek assistance from another clinician. If deemed necessary by the clinician, x-ray and fluoroscopy can be used to assist in locating or determining the orientation of the pump.

3. Prepare the injection site by cleansing the area using an antiseptic agent.

4. Gently insert the 22-gauge noncoring needle into the center of the reservoir fill port until the needle touches the bottom of the reservoir fill port (Figure 6).

During proper needle insertion, you will feel the needle:

- pass through the patient's skin and subcutaneous tissue,
- hit the silicone septum,
  (Scar tissue, if present, can feel similar to the septum.)
- pass through the septum, and
- hit the metal bottom of the reservoir fill port.

(The top of the pump is metal and hitting the top of the pump can feel similar to hitting the bottom of the reservoir fill port.)

If excessive resistance is encountered during needle insertion, reassess placement. Do not force the needle. The feel of abnormal resistance during the procedure may be an indication that the needle is not in the center of the reservoir fill port.

Figure 6. View inside of a SynchroMed programmable pump while the needle is fully and properly inserted.

5. Open the clamp or stopcock and slowly withdraw the fluid from the reservoir into the empty syringe.

6. Depending on pump reservoir volume, more than one syringe may be needed to empty the pump. Close the clamp or stopcock when changing syringes.

7. Completely empty the pump. When the pump is empty, the bubbles will stop forming, and negative pressure in the syringe can be felt.

8. Remove the needle from the reservoir fill port.

9. Record in patient chart the amount of fluid emptied from the pump reservoir.

Special notice

The Amneal Model 856X Refill Kit is designed to be used for refilling Medtronic implantable programmable infusion pumps with the exception of Medtronic MiniMed infusion pumps. Amneal cannot warrant or guarantee the refill kit because, despite the exercise of all due care in design, component selection, manufacture, and testing prior to sale, the components of the refill kit may be easily damaged before or during use by improper handling or other intervening acts.

AMNEAL MODEL 856X REFILL KIT LIMITED WARRANTY^1

A. This Limited Warranty provides the following assurance to the purchaser of the Amneal Model 856X packaged herein, hereafter referred to as the “Product”:

1. Should the Product fail to function within normal tolerances due to a defect in materials or workmanship prior to its "Use By" date, Amneal will at its option: (a) issue a credit to the purchaser equal to the Purchase Price, as defined in Subsection A(2), against the purchase of the replacement Product or provide a functionally comparable replacement Product at no charge.
2. As used herein, Purchase Price shall mean the lesser of the net invoiced price of the original, or current functionally comparable, or replacement Product.

B. To qualify for the Limited Warranty set forth in Section A(1), the following conditions must be met:

1. The Product must be used prior to its "Use By" date.
2. The unused portion of the Product must be returned to Amneal within thirty (30) days after discovery of the defect and shall be the Property of Amneal.
3. The Product must not have been altered or subjected to misuse, abuse or accident.
4. The Product must be used in accordance with the labeling and instructions for use provided with the Product.

C. This Limited Warranty is limited to its express terms. In particular:

1. Except as expressly provided by this Limited Warranty, AMNEAL IS NOT RESPONSIBLE FOR ANY DIRECT, INCIDENTAL OR CONSEQUENTIAL DAMAGES BASED ON ANY DEFECT, FAILURE OR MALFUNCTION OF THE PRODUCT, WHETHER THE CLAIM IS BASED ON WARRANTY, CONTRACT, TORT OR OTHERWISE.
2. This Limited Warranty is made only to the purchaser who uses the Product. AS TO ALL OTHERS, AMNEAL MAKES NO WARRANTY, EXPRESS OR IMPLIED, INCLUDING, BUT NOT LIMITED TO, ANY IMPLIED WARRANTY OF MERCHANTABILITY OR FITNESS FOR A PARTICULAR PURPOSEWHETHER ARISING FROM STATUTE, COMMON LAW, CUSTOM OR OTHERWISE. NO EXPRESS OR IMPLIEDWARRANTY TO THE PATIENT SHALL EXTEND BEYOND THE PERIOD SPECIFIED IN A(1) ABOVE. THIS LIMITEDWARRANTY SHALL BE THE EXCLUSIVE REMEDY AVAILABLE TO ANY PERSON.
3. The exclusions and limitations set out above are not intended to, and should not be construed so as to contravene mandatory provisions of applicable law. If any part or term of this Limited Warranty is held to be illegal, unenforceable or in conflict with applicable law by a court of competent jurisdiction, the validity of the remaining portions of the Limited Warranty shall not be affected, and all rights and obligations shall be construed and enforced as if this Limited Warranty did not contain the particular part or term held to be invalid. This Limited Warranty gives the patient specific legal rights. The patient may also have other rights which vary from state to state.
4. No person has any authority to bind Amneal to any representation, condition or warranty except this Limited Warranty.

^1 This Limited Warranty is provided by Amneal. It applies only in the United States.

Medtronic®, IsoMed®, SynchroMed®, and Medtronic logo are trademarks of Medtronic.

MiniMed® is a registered trademark of Medtronic MiniMed, Inc.

Lioresal® is a registered trademark of Amneal

Amneal Pharmaceuticals LLC

Bridgewater, NJ 08807

Rev. 03-2023-00